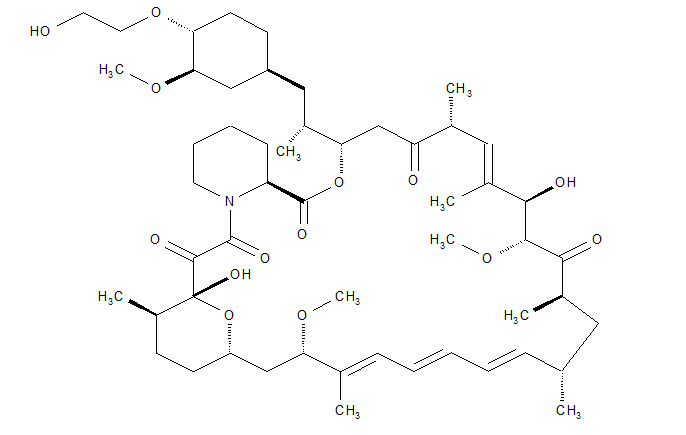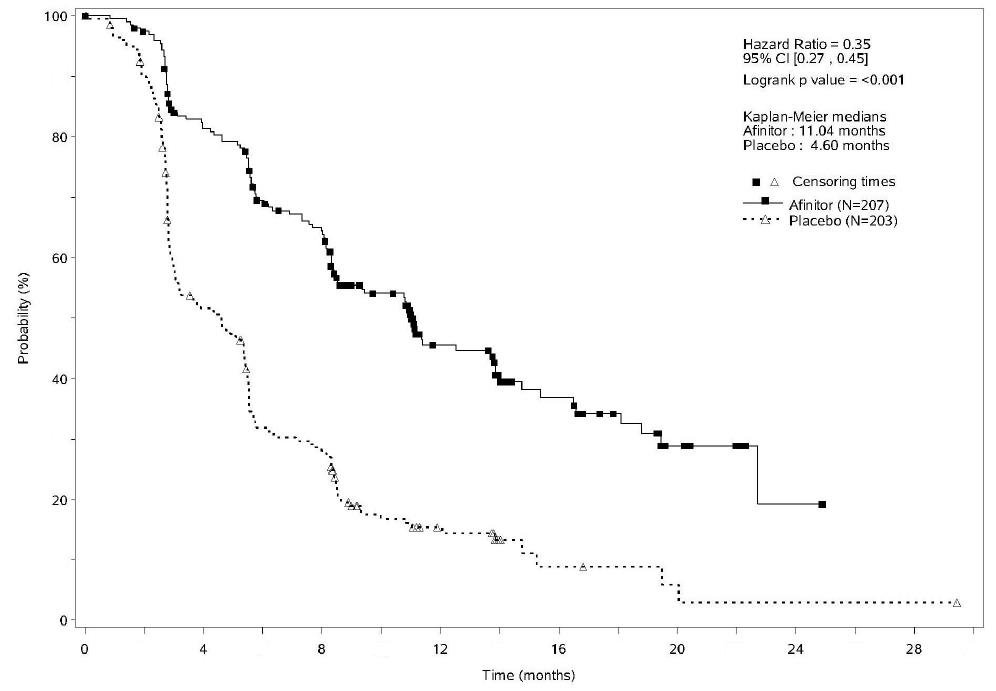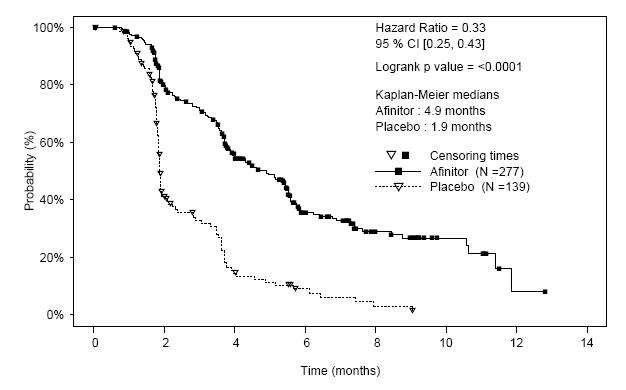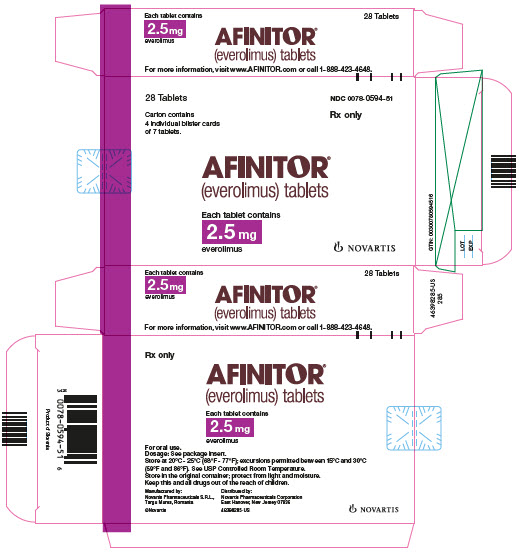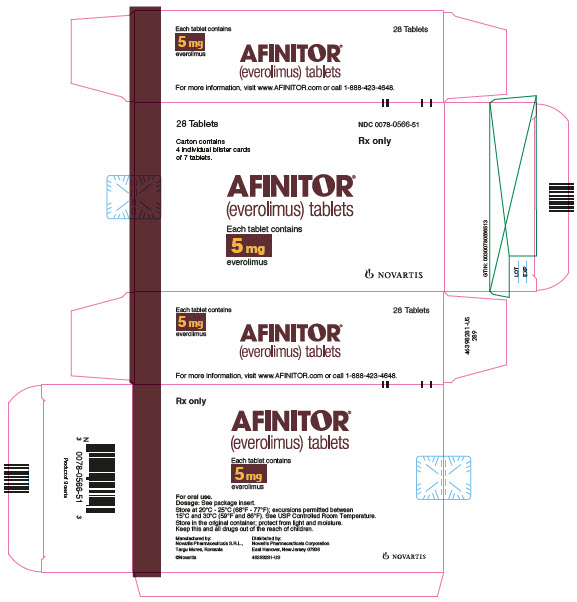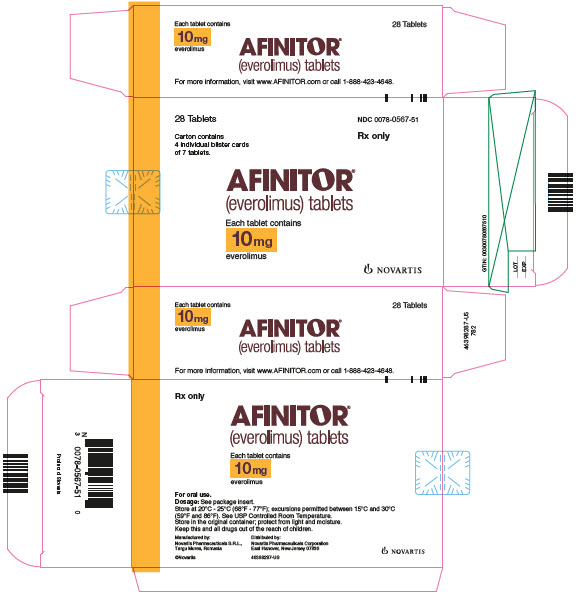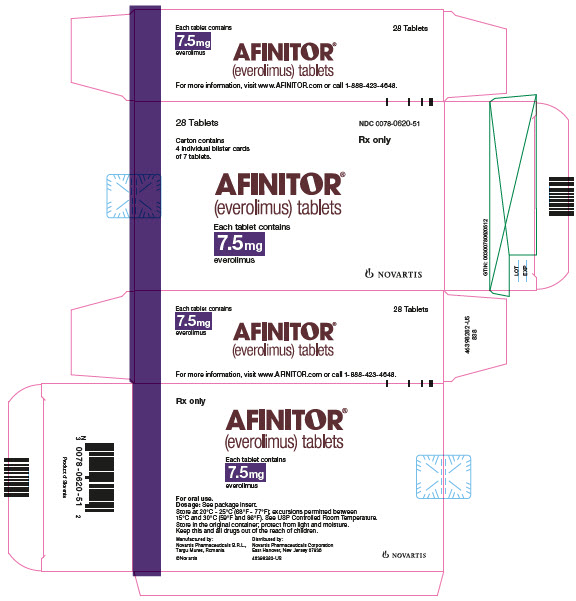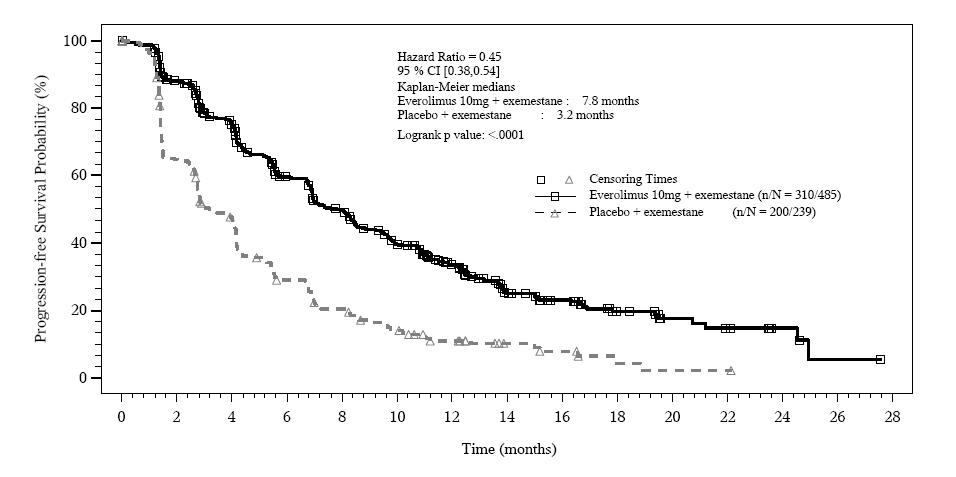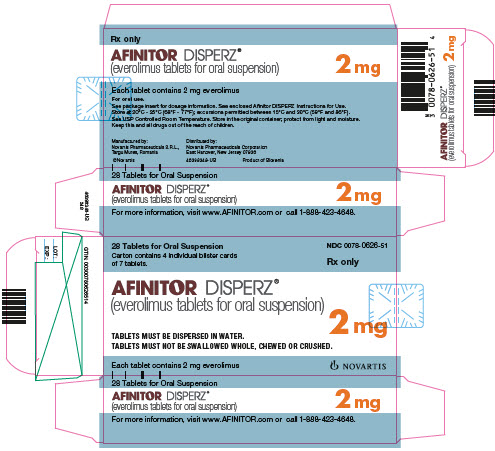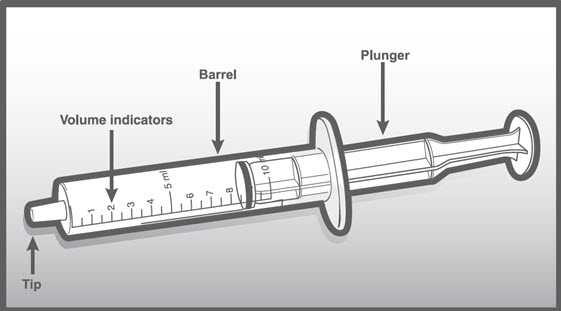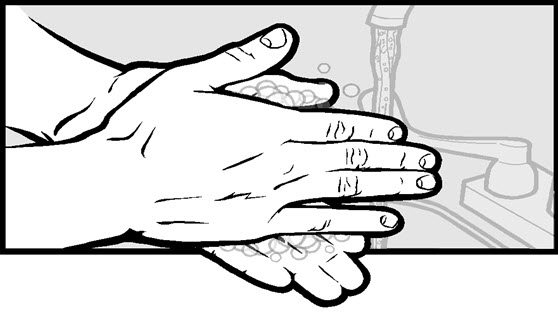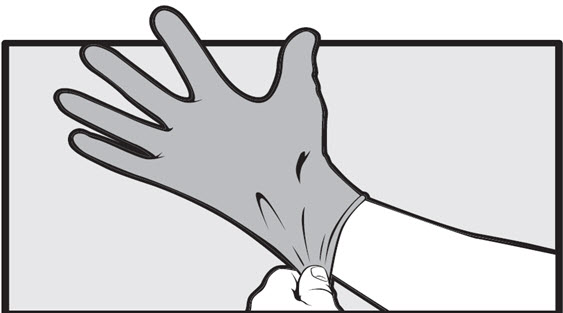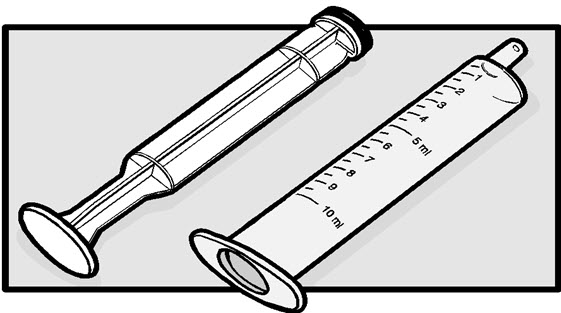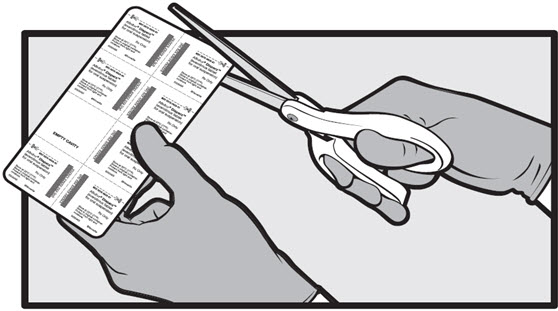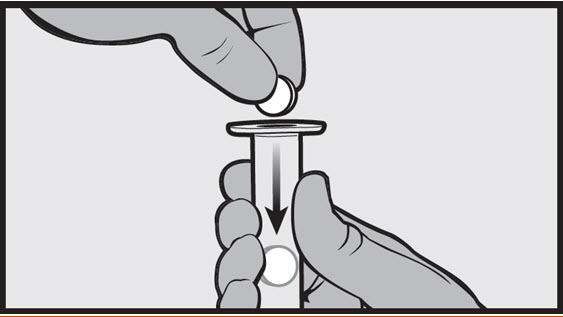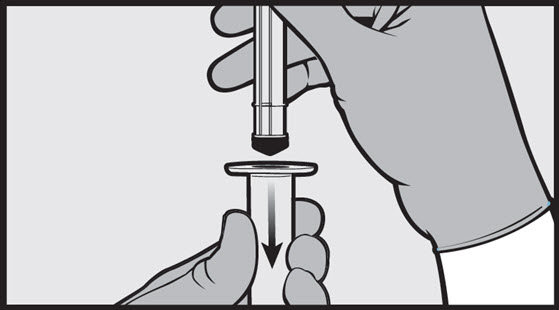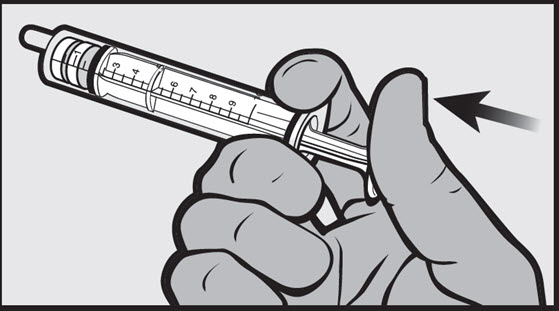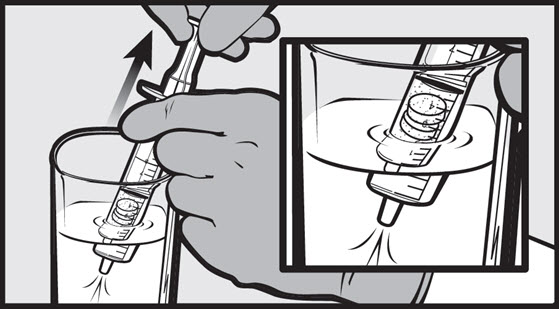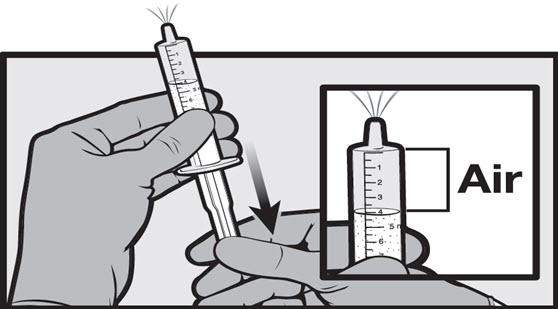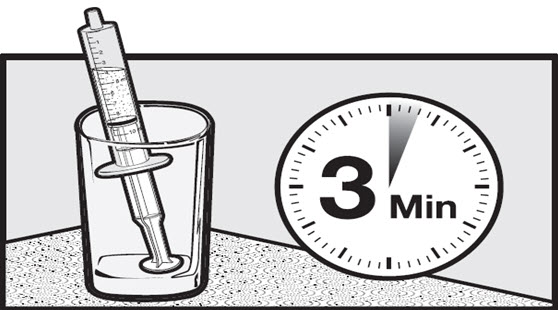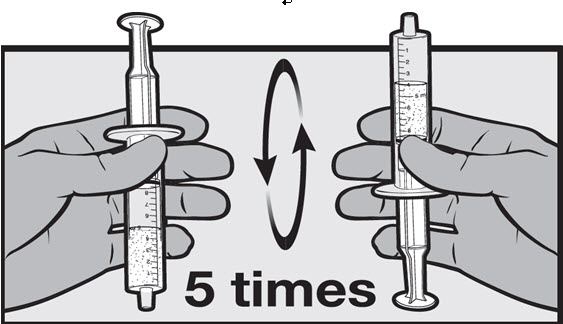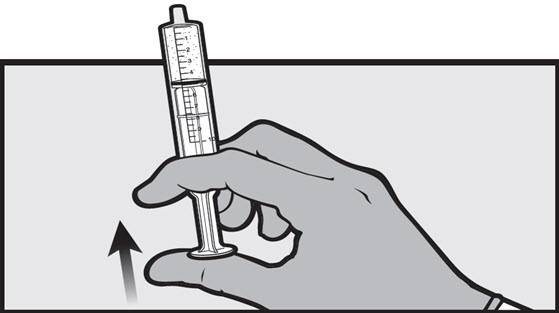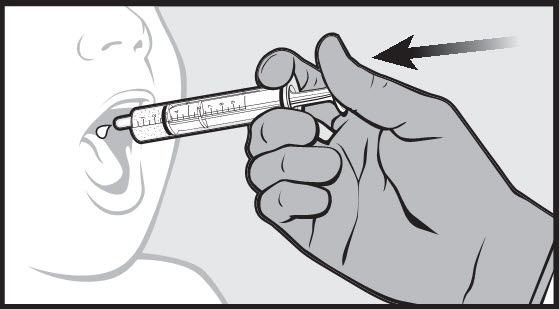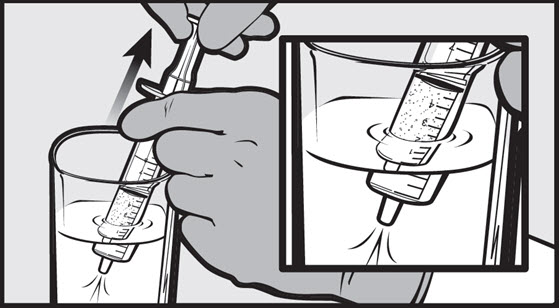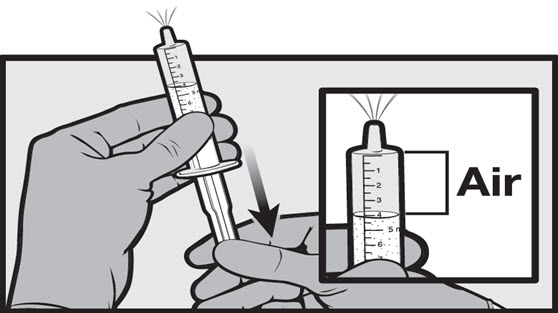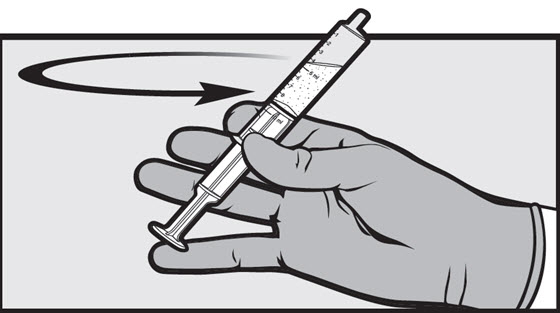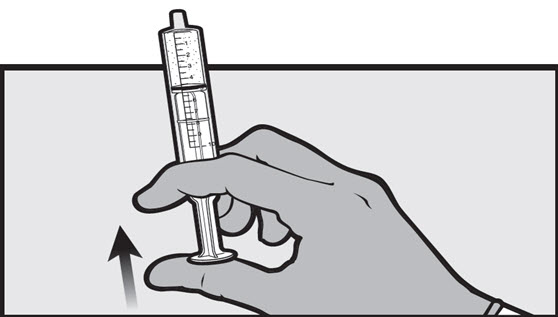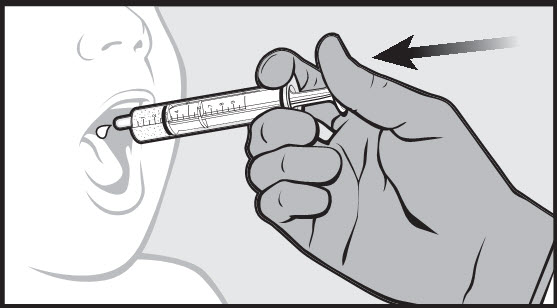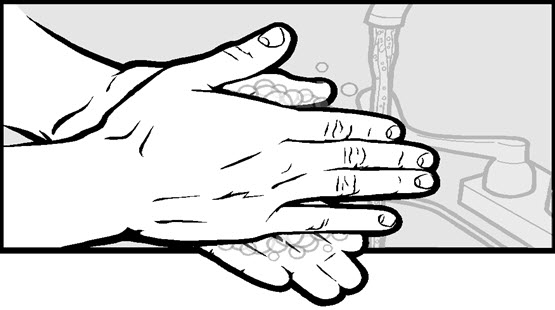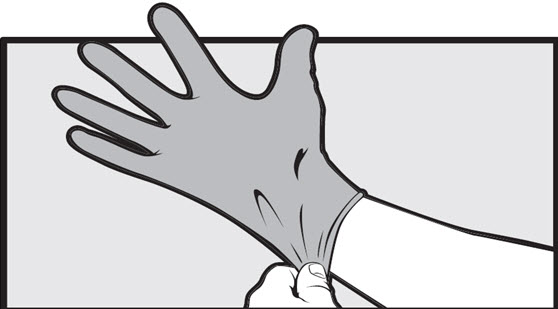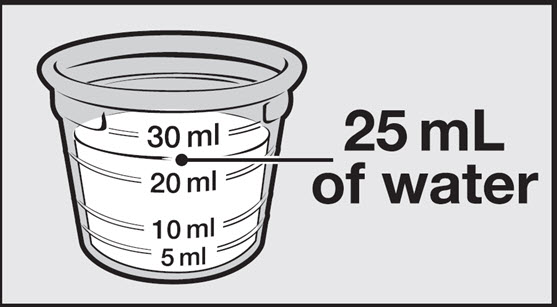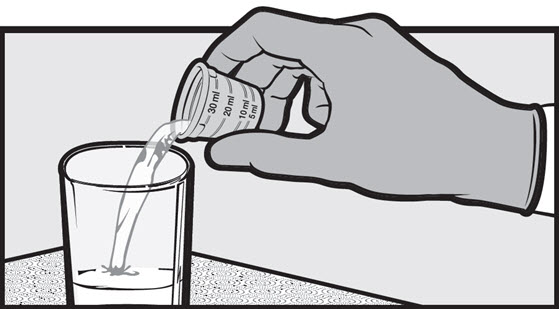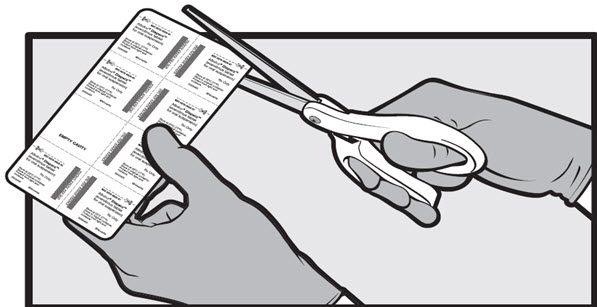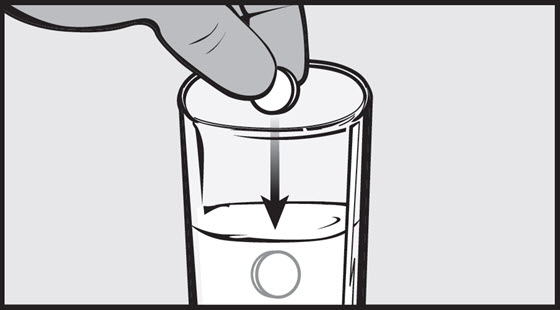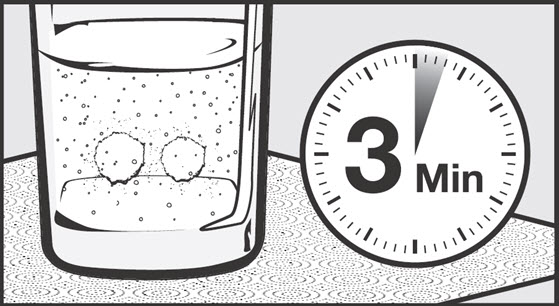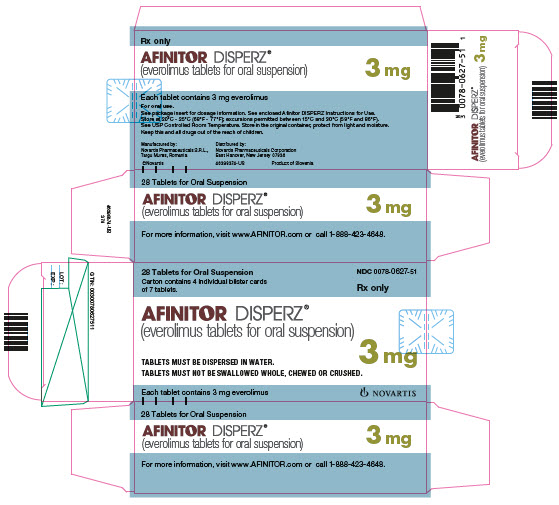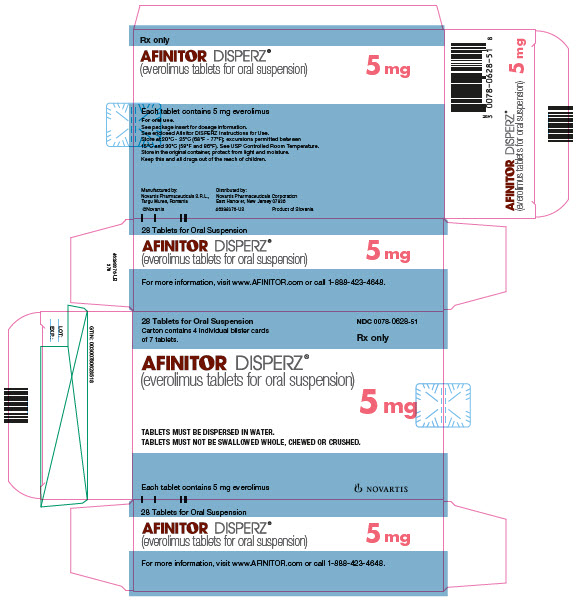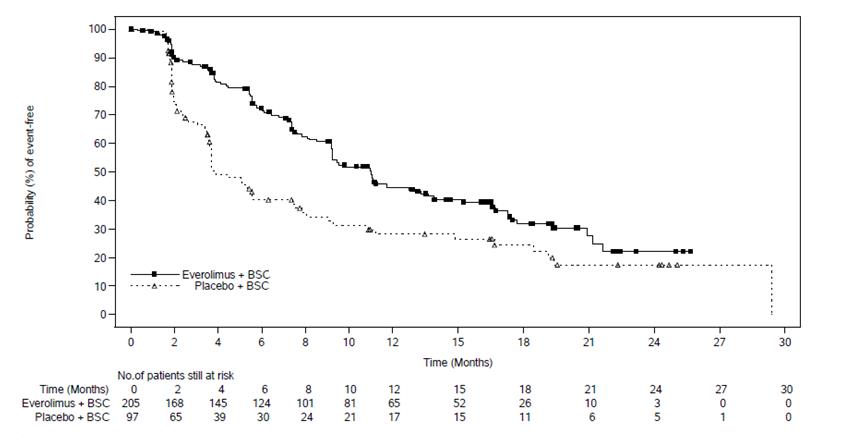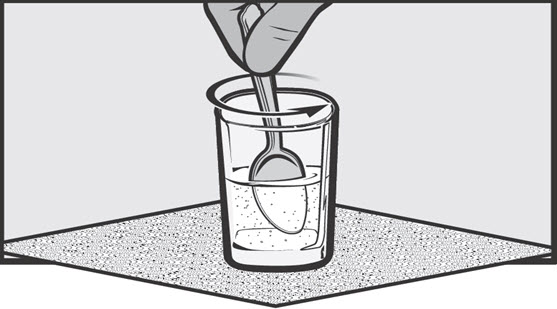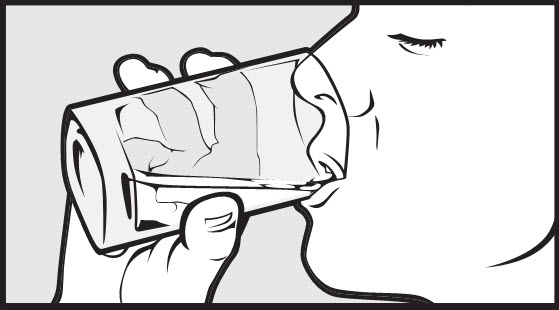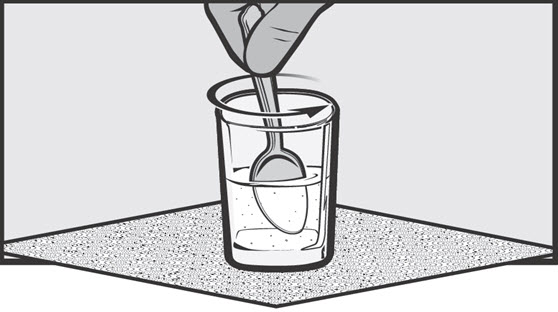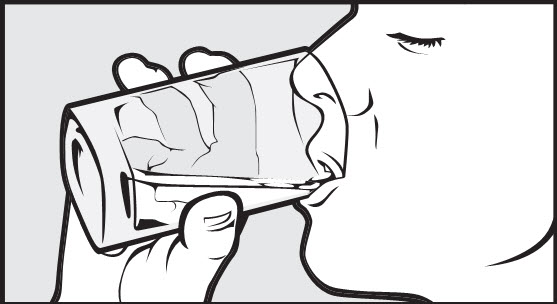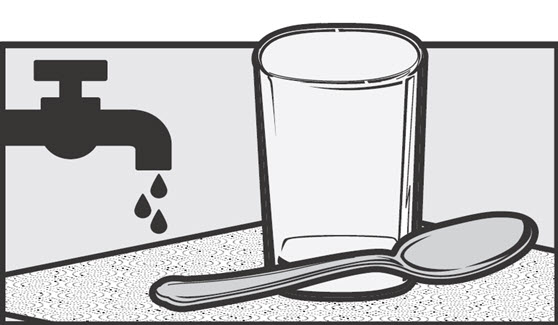 DRUG LABEL: Afinitor
NDC: 0078-0566 | Form: TABLET
Manufacturer: Novartis Pharmaceuticals Corporation
Category: prescription | Type: HUMAN PRESCRIPTION DRUG LABEL
Date: 20260212

ACTIVE INGREDIENTS: EVEROLIMUS 5 mg/1 1
INACTIVE INGREDIENTS: BUTYLATED HYDROXYTOLUENE; CROSPOVIDONE; HYPROMELLOSES; ANHYDROUS LACTOSE; LACTOSE MONOHYDRATE; MAGNESIUM STEARATE

HIGHLIGHTS OF PRESCRIBING INFORMATION

These highlights do not include all the information needed to use AFINITOR/AFINITOR DISPERZ safely and effectively. See full prescribing information for AFINITOR/AFINITOR DISPERZ.
AFINITOR® (everolimus) tablets, for oral use
AFINITOR DISPERZ® (everolimus tablets for oral suspension)
Initial U.S. Approval: 2009

RECENT MAJOR CHANGES

Warnings and Precautions, Radiation Sensitization and Radiation Recall (5.12) | 4/2021

1 INDICATIONS AND USAGE

AFINITOR is a kinase inhibitor indicated for the treatment of:

- Postmenopausal women with advanced hormone receptor-positive, HER2-negative breast cancer in combination with exemestane after failure of treatment with letrozole or anastrozole. (1.1)
- Adults with progressive neuroendocrine tumors of pancreatic origin (PNET) and adults with progressive, well-differentiated, non-functional neuroendocrine tumors (NET) of gastrointestinal (GI) or lung origin that are unresectable, locally advanced or metastatic.
  Limitations of Use: AFINITOR is not indicated for the treatment of patients with functional carcinoid tumors. (1.2)
- Adults with advanced renal cell carcinoma (RCC) after failure of treatment with sunitinib or sorafenib. (1.3)
- Adults with renal angiomyolipoma and tuberous sclerosis complex (TSC), not requiring immediate surgery. (1.4)

AFINITOR and AFINITOR DISPERZ are kinase inhibitors indicated for the treatment of adult and pediatric patients aged 1 year and older with TSC who have subependymal giant cell astrocytoma (SEGA) that requires therapeutic intervention but cannot be curatively resected. (1.5)

AFINITOR DISPERZ is a kinase inhibitor indicated for the adjunctive treatment of adult and pediatric patients aged 2 years and older with TSC-associated partial-onset seizures. (1.6)

2 DOSAGE AND ADMINISTRATION

Do not combine AFINITOR and AFINITOR DISPERZ to achieve the total daily dose. (2.1)

Modify the dose for patients with hepatic impairment or for patients taking drugs that inhibit or induce P-glycoprotein (P-gp) and CYP3A4. (2.1)

Breast Cancer:

- 10 mg orally once daily. (2.2)

NET:

- 10 mg orally once daily. (2.3)

RCC:

- 10 mg orally once daily. (2.4)

TSC-Associated Renal Angiomyolipoma:

- 10 mg orally once daily. (2.5)

TSC-Associated SEGA:

- 4.5 mg/m^2 orally once daily; adjust dose to attain trough concentrations of 5-15 ng/mL. (2.6, 2.8)

TSC-Associated Partial-Onset Seizures:

- 5 mg/m^2 orally once daily; adjust dose to attain trough concentrations of 5-15 ng/mL. (2.7, 2.8)

3 DOSAGE FORMS AND STRENGTHS

- AFINITOR: 2.5 mg, 5 mg, 7.5 mg, and 10 mg tablets (3)
- AFINITOR DISPERZ: 2 mg, 3 mg, and 5 mg tablets (3)

4 CONTRAINDICATIONS

Clinically significant hypersensitivity to everolimus or to other rapamycin derivatives. (4)

5 WARNINGS AND PRECAUTIONS

- Non-Infectious Pneumonitis: Monitor for clinical symptoms or radiological changes. Withhold or permanently discontinue based on severity. (2.9, 5.1)
- Infections: Monitor for signs and symptoms of infection. Withhold or permanently discontinue based on severity. (2.9, 5.2)
- Severe Hypersensitivity Reactions: Permanently discontinue for clinically significant hypersensitivity. (5.3)
- Angioedema: Patients taking concomitant angiotensin-converting-enzyme (ACE) inhibitors may be at increased risk for angioedema. Permanently discontinue for angioedema. (5.4, 7.2)
- Stomatitis: Initiate dexamethasone alcohol-free mouthwash when starting treatment. (5.5, 6.1)
- Renal Failure: Monitor renal function prior to treatment and periodically thereafter. (5.6)
- Risk of Impaired Wound Healing: Withhold for at least 1 week prior to elective surgery. Do not administer for at least 2 weeks following major surgery and until adequate wound healing. The safety of resumption of treatment after resolution of wound healing complications has not been established. (5.7)
- Geriatric Patients: Monitor and adjust dose for adverse reactions. (5.8)
- Metabolic Disorders: Monitor serum glucose and lipids prior to treatment and periodically thereafter. Withhold or permanently discontinue based on severity. (2.9, 5.9)
- Myelosuppression: Monitor hematologic parameters prior to treatment and periodically thereafter. Withhold or permanently discontinue based on severity. (2.9, 5.10)
- Risk of Infection or Reduced Immune Response with Vaccination: Avoid live vaccines and close contact with those who have received live vaccines. Complete recommended childhood vaccinations prior to starting treatment. (5.11)
- Radiation Sensitization and Radiation Recall: Severe radiation reactions may occur. (5.12, 6.2)
- Embryo-Fetal Toxicity: Can cause fetal harm. Advise patients of reproductive potential of the potential risk to a fetus and to use effective contraception. (5.13, 8.1, 8.3)

6 ADVERSE REACTIONS

- Breast cancer, NET, RCC: Most common adverse reactions (incidence ≥ 30%) include stomatitis, infections, rash, fatigue, diarrhea, edema, abdominal pain, nausea, fever, asthenia, cough, headache, and decreased appetite. (6.1)
- TSC-Associated Renal Angiomyolipoma: Most common adverse reaction (incidence ≥ 30%) is stomatitis. (6.1)
- TSC-Associated SEGA: Most common adverse reactions (incidence ≥ 30%) are stomatitis and respiratory tract infection. (6.1)
- TSC-Associated Partial-Onset Seizures: Most common adverse reaction (incidence ≥ 30%) is stomatitis. (6.1)

To report SUSPECTED ADVERSE REACTIONS, contact Novartis Pharmaceuticals Corporation at 1-888-669-6682 or FDA at 1-800-FDA-1088 or www.fda.gov/medwatch.

7 DRUG INTERACTIONS

- P-gp and strong CYP3A4 inhibitors: Avoid concomitant use. (2.11, 7.1)
- P-gp and moderate CYP3A4 inhibitors: Reduce the dose as recommended. (2.11, 7.1)
- P-gp and strong CYP3A4 inducers: Increase the dose as recommended. (2.12, 7.1)

8 USE IN SPECIFIC POPULATIONS

- For breast cancer, NET, RCC, or TSC-associated renal angiomyolipoma patients with hepatic impairment, reduce the dose. (2.10, 8.6)
- For patients with TSC-associated SEGA or TSC-associated partial-onset seizures and severe hepatic impairment, reduce the starting dose and adjust dose to attain target trough concentrations. (2.8, 2.10, 8.6)

FULL PRESCRIBING INFORMATION

1 INDICATIONS AND USAGE

1.1 Hormone Receptor-Positive, HER2-Negative Breast Cancer

AFINITOR® is indicated for the treatment of postmenopausal women with advanced hormone receptor-positive, HER2-negative breast cancer in combination with exemestane, after failure of treatment with letrozole or anastrozole.

1.2 Neuroendocrine Tumors (NET)

AFINITOR is indicated for the treatment of adult patients with progressive neuroendocrine tumors of pancreatic origin (PNET) with unresectable, locally advanced or metastatic disease.

AFINITOR is indicated for the treatment of adult patients with progressive, well-differentiated, non-functional NET of gastrointestinal (GI) or lung origin with unresectable, locally advanced or metastatic disease.

Limitations of Use: AFINITOR is not indicated for the treatment of patients with functional carcinoid tumors [see Clinical Studies (14.2)].

1.3 Renal Cell Carcinoma (RCC)

AFINITOR is indicated for the treatment of adult patients with advanced RCC after failure of treatment with sunitinib or sorafenib.

1.4 Tuberous Sclerosis Complex (TSC)-Associated Renal Angiomyolipoma

AFINITOR is indicated for the treatment of adult patients with renal angiomyolipoma and TSC, not requiring immediate surgery.

1.5 Tuberous Sclerosis Complex (TSC)-Associated Subependymal Giant Cell Astrocytoma (SEGA)

AFINITOR and AFINITOR DISPERZ® are indicated in adult and pediatric patients aged 1 year and older with TSC for the treatment of SEGA that requires therapeutic intervention but cannot be curatively resected.

1.6 Tuberous Sclerosis Complex (TSC)-Associated Partial-Onset Seizures

AFINITOR DISPERZ is indicated for the adjunctive treatment of adult and pediatric patients aged 2 years and older with TSC-associated partial-onset seizures.

2 DOSAGE AND ADMINISTRATION

2.1 Important Dosage Information

- AFINITOR and AFINITOR DISPERZ are two different dosage forms. Select the recommended dosage form based on the indication [see Indications and Usage (1)]. Do not combine AFINITOR and AFINITOR DISPERZ to achieve the total dose.
- Modify the dosage for patients with hepatic impairment or for patients taking drugs that inhibit or induce P-glycoprotein (P-gp) and CYP3A4 [see Dosage and Administration (2.10, 2.11, 2.12)].

2.2 Recommended Dosage for Hormone Receptor-Positive, HER2-Negative Breast Cancer

The recommended dosage of AFINITOR is 10 mg orally once daily until disease progression or unacceptable toxicity.

2.3 Recommended Dosage for Neuroendocrine Tumors (NET)

The recommended dosage of AFINITOR is 10 mg orally once daily until disease progression or unacceptable toxicity.

2.4 Recommended Dosage for Renal Cell Carcinoma (RCC)

The recommended dosage of AFINITOR is 10 mg orally once daily until disease progression or unacceptable toxicity.

2.5 Recommended Dosage for Tuberous Sclerosis Complex (TSC)-Associated Renal Angiomyolipoma

The recommended dosage of AFINITOR is 10 mg orally once daily until disease progression or unacceptable toxicity.

2.6 Recommended Dosage for Tuberous Sclerosis Complex (TSC)-Associated Subependymal Giant Cell Astrocytoma (SEGA)

The recommended starting dosage of AFINITOR/AFINITOR DISPERZ is 4.5 mg/m^2 orally once daily until disease progression or unacceptable toxicity [see Dosage and Administration (2.8)].

2.7 Recommended Dosage for Tuberous Sclerosis Complex (TSC)-Associated Partial-Onset Seizures

The recommended starting dosage of AFINITOR DISPERZ is 5 mg/m^2 orally once daily until disease progression or unacceptable toxicity [see Dosage and Administration (2.8)].

2.8 Therapeutic Drug Monitoring (TDM) and Dose Titration for Tuberous Sclerosis Complex (TSC)-Associated Subependymal Giant Cell Astrocytoma (SEGA) and TSC-Associated Partial-Onset Seizures

- Monitor everolimus whole blood trough concentrations at time points recommended in Table 1.
- Titrate the dose to attain trough concentrations of 5 ng/mL to 15 ng/mL.
- Adjust the dose using the following equation:

New dose* = current dose x (target concentration divided by current concentration)

*The maximum dose increment at any titration must not exceed 5 mg. Multiple dose titrations may be required to attain the target trough concentration.

- When possible, use the same assay and laboratory for TDM throughout treatment.

Table 1: Recommended Timing of Therapeutic Drug Monitoring
Event | When to Assess Trough Concentrations After Event
Initiation of AFINITOR/AFINITOR DISPERZ | 1 to 2 weeks
Modification of AFINITOR/AFINITOR DISPERZ dose | 1 to 2 weeks
Switch between AFINITOR and AFINITOR DISPERZ | 1 to 2 weeks
Initiation or discontinuation of P-gp and moderate CYP3A4 inhibitor | 2 weeks
Initiation or discontinuation of P-gp and strong CYP3A4 inducer | 2 weeks
Change in hepatic function | 2 weeks
Stable dose with changing body surface area (BSA) | Every 3 to 6 months
Stable dose with stable BSA | Every 6 to 12 months
Abbreviation: P-gp, P-glycoprotein.

2.9 Dosage Modifications for Adverse Reactions

Table 2 summarizes recommendations for dosage modifications of AFINITOR/AFINITOR DISPERZ for the management of adverse reactions.

Table 2: Recommended Dosage Modifications for AFINITOR/AFINITOR DISPERZ for Adverse Reactions
Adverse Reaction | Severity | Dosage Modification
Non-infectious pneumonitis [see Warnings and Precautions (5.1)] | Grade 2 | Withhold until improvement to Grade 0 or 1. Resume at 50% of previous dose; change to every other day dosing if the reduced dose is lower than the lowest available strength. Permanently discontinue if toxicity does not resolve or improve to Grade 1 within 4 weeks.
 | Grade 3 | Withhold until improvement to Grade 0 or 1. Resume at 50% of previous dose; change to every other day dosing if the reduced dose is lower than the lowest available strength. If toxicity recurs at Grade 3, permanently discontinue.
 | Grade 4 | Permanently discontinue.
Stomatitis [see Warnings and Precautions (5.5)] | Grade 2 | Withhold until improvement to Grade 0 or 1. Resume at same dose. If recurs at Grade 2, withhold until improvement to Grade 0 or 1. Resume at 50% of previous dose; change to every other day dosing if the reduced dose is lower than the lowest available strength.
 | Grade 3 | Withhold until improvement to Grade 0 or 1. Resume at 50% of previous dose; change to every other day dosing if the reduced dose is lower than the lowest available strength.
 | Grade 4 | Permanently discontinue.
Metabolic events (e.g., hyperglycemia, dyslipidemia) [see Warnings and Precautions (5.9)] | Grade 3 | Withhold until improvement to Grade 0, 1, or 2. Resume at 50% of previous dose; change to every other day dosing if the reduced dose is lower than the lowest available strength.
 | Grade 4 | Permanently discontinue.
Other non-hematologic toxicities | Grade 2 | If toxicity becomes intolerable, withhold until improvement to Grade 0 or 1. Resume at same dose. If toxicity recurs at Grade 2, withhold until improvement to Grade 0 or 1. Resume at 50% of previous dose; change to every other day dosing if the reduced dose is lower than the lowest available strength.
 | Grade 3 | Withhold until improvement to Grade 0 or 1. Consider resuming at 50% of previous dose; change to every other day dosing if the reduced dose is lower than the lowest available strength. If recurs at Grade 3, permanently discontinue.
 | Grade 4 | Permanently discontinue.
Thrombocytopenia [see Warnings and Precautions (5.10)] | Grade 2 | Withhold until improvement to Grade 0 or 1. Resume at same dose.
 | Grade 3 OR Grade 4 | Withhold until improvement to Grade 0 or 1. Resume at 50% of previous dose; change to every other day dosing if the reduced dose is lower than the lowest available strength.
Neutropenia [see Warnings and Precautions (5.10)] | Grade 3 | Withhold until improvement to Grade 0, 1, or 2. Resume at same dose.
 | Grade 4 | Withhold until improvement to Grade 0, 1, or 2. Resume at 50% of previous dose; change to every other day dosing if the reduced dose is lower than the lowest available strength.
Febrile neutropenia [see Warnings and Precautions (5.10)] | Grade 3 | Withhold until improvement to Grade 0, 1, or 2, and no fever. Resume at 50% of previous dose; change to every other day dosing if the reduced dose is lower than the lowest available strength.
 | Grade 4 | Permanently discontinue.

2.10 Dosage Modifications for Hepatic Impairment

The recommended dosages of AFINITOR/AFINITOR DISPERZ for patients with hepatic impairment are described in Table 3 [see Use in Specific Populations (8.6)]:

Table 3: Recommended Dosage Modifications for Patients With Hepatic Impairment
Indication | Dose Modification for AFINITOR/AFINITOR DISPERZ
Breast Cancer, NET, RCC, and TSC-Associated Renal Angiomyolipoma | - Mild hepatic impairment (Child-Pugh class A) – 7.5 mg orally once daily; decrease the dose to 5 mg orally once daily if a dose of 7.5 mg once daily is not tolerated. - Moderate hepatic impairment (Child-Pugh class B) – 5 mg orally once daily; decrease the dose to 2.5 mg orally once daily if a dose of 5 mg once daily is not tolerated. - Severe hepatic impairment (Child-Pugh class C) – 2.5 mg orally once daily if the desired benefit outweighs the risk; do not exceed a dose of 2.5 mg once daily.
TSC-Associated SEGA and TSC- Associated Partial-Onset Seizures | - Severe hepatic impairment (Child-Pugh class C) – 2.5 mg/m^2 orally once daily. - Adjust dose based on everolimus trough concentrations as recommended [see Dosage and Administration (2.8)].
Abbreviations: NET, Neuroendocrine Tumors; RCC, Renal Cell Carcinoma; SEGA, Subependymal Giant Cell Astrocytoma; TSC, Tuberous Sclerosis Complex.

2.11 Dosage Modifications for P-gp and CYP3A4 Inhibitors

- Avoid the concomitant use of P-gp and strong CYP3A4 inhibitors [see Drug Interactions (7.1)].
- Avoid ingesting grapefruit and grapefruit juice.
- Reduce the dose for patients taking AFINITOR/AFINITOR DISPERZ with a P-gp and moderate CYP3A4 inhibitor as recommended in Table 4 [see Drug Interactions (7.1), Clinical Pharmacology (12.3)].

Table 4: Recommended Dosage Modifications for Concurrent Use of AFINITOR/AFINITOR DISPERZ With a P-gp and Moderate CYP3A4 Inhibitor
Indication | Dose Modification for AFINITOR/AFINITOR DISPERZ
Breast Cancer, NET, RCC, and TSC-Associated Renal Angiomyolipoma | - Reduce dose to 2.5 mg once daily. - May increase dose to 5 mg once daily if tolerated. - Resume dose administered prior to inhibitor initiation, once the inhibitor is discontinued for 3 days.
TSC-Associated SEGA and TSC- Associated Partial-Onset Seizures | - Reduce the daily dose by 50%. - Change to every other day dosing if the reduced dose is lower than the lowest available strength. - Resume dose administered prior to inhibitor initiation, once the inhibitor is discontinued for 3 days. - Assess trough concentrations when initiating and discontinuing the inhibitor [see Dosage and Administration (2.8)].

2.12 Dosage Modifications for P-gp and CYP3A4 Inducers

- Avoid concomitant use of St. John’s Wort (Hypericum perforatum).
- Increase the dose for patients taking AFINITOR/AFINITOR DISPERZ with a P-gp and strong CYP3A4 inducer as recommended in Table 5 [see Drug Interactions (7.1), Clinical Pharmacology (12.3)].

Table 5: Recommended Dosage Modifications for Concurrent Use of AFINITOR/AFINITOR DISPERZ With P-gp and Strong CYP3A4 Inducers
Indication | Dose Modification for AFINITOR/AFINITOR DISPERZ
Breast Cancer, NET, RCC, and TSC-Associated Renal Angiomyolipoma | - Avoid coadministration where alternatives exist. - If coadministration cannot be avoided, double the daily dose using increments of 5 mg or less. Multiple increments may be required. - Resume the dose administered prior to inducer initiation, once an inducer is discontinued for 5 days.
TSC-Associated SEGA and TSC- Associated Partial-Onset Seizures | - Double the daily dose using increments of 5 mg or less. Multiple increments may be required. - Addition of another strong CYP3A4 inducer in a patient already receiving treatment with a strong CYP3A4 inducer may not require additional dosage modification. - Assess trough concentrations when initiating and discontinuing the inducer [see Dosage and Administration (2.8)]. - Resume the dose administered before starting any inducer, once all inducers are discontinued for 5 days.

2.13 Administration and Preparation

- Administer AFINITOR/AFINITOR DISPERZ at the same time each day.
- Administer AFINITOR/AFINITOR DISPERZ consistently either with or without food [see Clinical Pharmacology (12.3)].
- If a dose of AFINITOR/AFINITOR DISPERZ is missed, it can be administered up to 6 hours after the time it is normally administered. After more than 6 hours, the dose should be skipped for that day. The next day, AFINITOR/AFINITOR DISPERZ should be administered at its usual time. Double doses should not be administered to make up for the dose that was missed.

AFINITOR

- AFINITOR should be swallowed whole with a glass of water. Do not break or crush tablets.

AFINITOR DISPERZ

- Wear gloves to avoid possible contact with everolimus when preparing suspensions of AFINITOR DISPERZ for another person.
- Administer as a suspension only.
- Administer suspension immediately after preparation. Discard suspension if not administered within 60 minutes after preparation.
- Prepare suspension in water only.

Using an Oral Syringe to Prepare Oral Suspension:

- Place the prescribed dose into a 10-mL syringe. Do not exceed a total of 10 mg per syringe. If higher doses are required, prepare an additional syringe. Do not break or crush tablets.
- Draw approximately 5 mL of water and 4 mL of air into the syringe.
- Place the filled syringe into a container (tip up) for 3 minutes, until the tablets are in suspension.
- Gently invert the syringe 5 times immediately prior to administration.
- After administration of the prepared suspension, draw approximately 5 mL of water and 4 mL of air into the same syringe, and swirl the contents to suspend remaining particles. Administer the entire contents of the syringe.

Using a Small Drinking Glass to Prepare Oral Suspension:

- Place the prescribed dose into a small drinking glass (maximum size 100 mL) containing approximately 25 mL of water. Do not exceed a total of 10 mg per glass. If higher doses are required, prepare an additional glass. Do not break or crush tablets.
- Allow 3 minutes for suspension to occur.
- Stir the contents gently with a spoon, immediately prior to drinking.
- After administration of the prepared suspension, add 25 mL of water and stir with the same spoon to re-suspend remaining particles. Administer the entire contents of the glass.

3 DOSAGE FORMS AND STRENGTHS

AFINITOR

Tablets, white to slightly yellow and elongated with a bevelled edge:

- 2.5 mg: engraved with “LCL” on one side and “NVR” on the other.
- 5 mg: engraved with “5” on one side and “NVR” on the other.
- 7.5 mg: engraved with “7P5” on one side and “NVR” on the other.
- 10 mg: engraved with “UHE” on one side and “NVR” on the other.

AFINITOR DISPERZ

Tablets for oral suspension, white to slightly yellowish, round, and flat with a bevelled edge:

- 2 mg: engraved with “D2” on one side and “NVR” on the other.
- 3 mg: engraved with “D3” on one side and “NVR” on the other.
- 5 mg: engraved with “D5” on one side and “NVR” on the other.

4 CONTRAINDICATIONS

AFINITOR/AFINITOR DISPERZ is contraindicated in patients with clinically significant hypersensitivity to everolimus or to other rapamycin derivatives [see Warnings and Precautions (5.3)].

5 WARNINGS AND PRECAUTIONS

5.1 Non-infectious Pneumonitis

Non-infectious pneumonitis is a class effect of rapamycin derivatives. Non-infectious pneumonitis was reported in up to 19% of patients treated with AFINITOR/AFINITOR DISPERZ in clinical trials, some cases were reported with pulmonary hypertension (including pulmonary arterial hypertension) as a secondary event. The incidence of Grade 3 and 4 non-infectious pneumonitis was up to 4% and up to 0.2%, respectively [see Adverse Reactions (6.1)]. Fatal outcomes have been observed.

Consider a diagnosis of non-infectious pneumonitis in patients presenting with non-specific respiratory signs and symptoms. Consider opportunistic infections, such as pneumocystis jiroveci pneumonia (PJP) in the differential diagnosis. Advise patients to report promptly any new or worsening respiratory symptoms.

Continue AFINITOR/AFINITOR DISPERZ without dose alteration in patients who develop radiological changes suggestive of non-infectious pneumonitis and have few or no symptoms. Imaging appears to overestimate the incidence of clinical pneumonitis.

For Grade 2 to 4 non-infectious pneumonitis, withhold or permanently discontinue AFINITOR/AFINITOR DISPERZ based on severity [see Dosage and Administration (2.9)]. Corticosteroids may be indicated until clinical symptoms resolve. Administer prophylaxis for PJP when concomitant use of corticosteroids or other immunosuppressive agents are required. The development of pneumonitis has been reported even at a reduced dose.

5.2 Infections

AFINITOR/AFINITOR DISPERZ has immunosuppressive properties and may predispose patients to bacterial, fungal, viral, or protozoal infections, including infections with opportunistic pathogens [see Adverse Reactions (6.1)]. Localized and systemic infections, including pneumonia, mycobacterial infections, other bacterial infections, invasive fungal infections (e.g., aspergillosis, candidiasis, or PJP), and viral infections (e.g., reactivation of hepatitis B virus) have occurred. Some of these infections have been severe (e.g., sepsis, septic shock, or resulting in multisystem organ failure) or fatal. The incidence of Grade 3 and 4 infections was up to 10% and up to 3%, respectively. The incidence of serious infections was reported at a higher frequency in patients < 6 years of age [see Use in Specific Populations (8.4)].

Complete treatment of preexisting invasive fungal infections prior to starting treatment. Monitor for signs and symptoms of infection. Withhold or permanently discontinue AFINITOR/AFINITOR DISPERZ based on severity of infection [see Dosage and Administration (2.9)].

Administer prophylaxis for PJP when concomitant use of corticosteroids or other immunosuppressive agents are required.

5.3 Severe Hypersensitivity Reactions

Hypersensitivity reactions to AFINITOR/AFINITOR DISPERZ have been observed and include anaphylaxis, dyspnea, flushing, chest pain, and angioedema (e.g., swelling of the airways or tongue, with or without respiratory impairment) [see Contraindications (4)]. The incidence of Grade 3 hypersensitivity reactions was up to 1%. Permanently discontinue AFINITOR/AFINITOR DISPERZ for the development of clinically significant hypersensitivity.

5.4 Angioedema With Concomitant Use of Angiotensin-Converting Enzyme (ACE) Inhibitors

Patients taking concomitant ACE inhibitors with AFINITOR/AFINITOR DISPERZ may be at increased risk for angioedema (e.g., swelling of the airways or tongue, with or without respiratory impairment). In a pooled analysis of randomized double-blind oncology clinical trials, the incidence of angioedema in patients taking AFINITOR with an ACE inhibitor was 6.8% compared to 1.3% in the control arm with an ACE inhibitor. Permanently discontinue AFINITOR/AFINITOR DISPERZ for angioedema.

5.5 Stomatitis

Stomatitis, including mouth ulcers and oral mucositis, has occurred in patients treated with AFINITOR/AFINITOR DISPERZ at an incidence ranging from 44% to 78% across clinical trials. Grades 3-4 stomatitis was reported in 4% to 9% of patients [see Adverse Reactions (6.1)]. Stomatitis most often occurs within the first 8 weeks of treatment. When starting AFINITOR/AFINITOR DISPERZ, initiating dexamethasone alcohol-free oral solution as a swish and spit mouthwash reduces the incidence and severity of stomatitis [see Adverse Reactions (6.1)]. If stomatitis does occur, mouthwashes and/or other topical treatments are recommended. Avoid alcohol-, hydrogen peroxide-, iodine-, or thyme- containing products, as they may exacerbate the condition. Do not administer antifungal agents, unless fungal infection has been diagnosed.

5.6 Renal Failure

Cases of renal failure (including acute renal failure), some with a fatal outcome, have occurred in patients taking AFINITOR. Elevations of serum creatinine and proteinuria have been reported in patients taking AFINITOR/AFINITOR DISPERZ [see Adverse Reactions (6.1)]. The incidence of Grade 3 and 4 elevations of serum creatinine was up to 2% and up to 1%, respectively. The incidence of Grade 3 and 4 proteinuria was up to 1% and up to 0.5%, respectively. Monitor renal function prior to starting AFINITOR/AFINITOR DISPERZ and annually thereafter. Monitor renal function at least every 6 months in patients who have additional risk factors for renal failure.

5.7 Risk of Impaired Wound Healing

Impaired wound healing can occur in patients who receive drugs that inhibit the VEGF signaling pathway. Therefore, AFINITOR/AFINITOR DISPERZ have the potential to adversely affect wound healing.

Withhold AFINITOR/AFINITOR DISPERZ for at least 1 week prior to elective surgery. Do not administer for at least 2 weeks following major surgery and until adequate wound healing. The safety of resumption of treatment upon resolution of wound healing complications has not been established.

5.8 Geriatric Patients

In the randomized hormone receptor-positive, HER2-negative breast cancer study (BOLERO-2), the incidence of deaths due to any cause within 28 days of the last AFINITOR dose was 6% in patients ≥ 65 years of age compared to 2% in patients < 65 years of age. Adverse reactions leading to permanent treatment discontinuation occurred in 33% of patients ≥ 65 years of age compared to 17% in patients < 65 years of age. Careful monitoring and appropriate dose adjustments for adverse reactions are recommended [see Dosage and Administration (2.9), Use in Specific Populations (8.5)].

5.9 Metabolic Disorders

Hyperglycemia, hypercholesterolemia, and hypertriglyceridemia have been reported in patients taking AFINITOR/AFINITOR DISPERZ at an incidence up to 75%, 86%, and 73%, respectively. The incidence of these Grade 3 and 4 laboratory abnormalities was up to 15% and up to 0.4%, respectively [see Adverse Reactions (6.1)]. In non-diabetic patients, monitor fasting serum glucose prior to starting AFINITOR/AFINITOR DISPERZ and annually thereafter. In diabetic patients, monitor fasting serum glucose more frequently as clinically indicated. Monitor lipid profile prior to starting AFINITOR/AFINITOR DISPERZ and annually thereafter. When possible, achieve optimal glucose and lipid control prior to starting AFINITOR/AFINITOR DISPERZ. For Grade 3 to 4 metabolic events, withhold or permanently discontinue AFINITOR/AFINITOR DISPERZ based on severity [see Dosage and Administration (2.9)].

5.10 Myelosuppression

Anemia, lymphopenia, neutropenia, and thrombocytopenia have been reported in patients taking AFINITOR/AFINITOR DISPERZ. The incidence of these Grade 3 and 4 laboratory abnormalities was up to 16% and up to 2%, respectively [see Adverse Reactions (6.1)]. Monitor complete blood count (CBC) prior to starting AFINITOR/AFINITOR DISPERZ every 6 months for the first year of treatment and annually thereafter. Withhold or permanently discontinue AFINITOR/AFINITOR DISPERZ based on severity [see Dosage and Administration (2.9)].

5.11 Risk of Infection or Reduced Immune Response With Vaccination

The safety of immunization with live vaccines during AFINITOR/AFINITOR DISPERZ therapy has not been studied. Due to the potential increased risk of infection, avoid the use of live vaccines and close contact with individuals who have received live vaccines during treatment with AFINITOR/AFINITOR DISPERZ. Due to the potential increased risk of infection or reduced immune response with vaccination, complete the recommended childhood series of vaccinations according to American Council on Immunization Practices (ACIP) guidelines prior to the start of therapy. An accelerated vaccination schedule may be appropriate.

5.12 Radiation Sensitization and Radiation Recall

Radiation sensitization and recall, in some cases severe, involving cutaneous and visceral organs (including radiation esophagitis and pneumonitis) have been reported in patients treated with radiation prior to, during, or subsequent to AFINITOR/AFINITOR DISPERZ treatment [see Adverse Reactions (6.2)].

Monitor patients closely when AFINITOR/AFINITOR DISPERZ is administered during or sequentially with radiation treatment.

5.13 Embryo-Fetal Toxicity

Based on animal studies and the mechanism of action, AFINITOR/AFINITOR DISPERZ can cause fetal harm when administered to a pregnant woman. In animal studies, everolimus caused embryo-fetal toxicities in rats when administered during the period of organogenesis at maternal exposures that were lower than human exposures at the clinical dose of 10 mg once daily. Advise pregnant women of the potential risk to a fetus. Advise female patients of reproductive potential to avoid becoming pregnant and to use effective contraception during treatment with AFINITOR/AFINITOR DISPERZ and for 8 weeks after the last dose. Advise male patients with female partners of reproductive potential to use effective contraception during treatment with AFINITOR/AFINITOR DISPERZ and for 4 weeks after the last dose [see Use in Specific Populations (8.1, 8.3)].

6 ADVERSE REACTIONS

The following serious adverse reactions are described elsewhere in the labeling:

- Non-Infectious Pneumonitis [see Warnings and Precautions (5.1)]
- Infections [see Warnings and Precautions (5.2)]
- Severe Hypersensitivity Reactions [see Warnings and Precautions (5.3)]
- Angioedema with Concomitant Use of ACE inhibitors [see Warnings and Precautions (5.4)]
- Stomatitis [see Warnings and Precautions (5.5)]
- Renal Failure [see Warnings and Precautions (5.6)]
- Impaired Wound Healing [see Warnings and Precautions (5.7)]
- Metabolic Disorders [see Warnings and Precautions (5.9)]
- Myelosuppression [see Warnings and Precautions (5.10)]
- Radiation Sensitization and Radiation Recall [see Warnings and Precautions (5.12)]

6.1 Clinical Trials Experience

Because clinical trials are conducted under widely varying conditions, the adverse reaction rates observed cannot be directly compared to rates in other trials and may not reflect the rates observed in clinical practice.

Hormone Receptor-Positive, HER2-Negative Breast Cancer

The safety of AFINITOR (10 mg orally once daily) in combination with exemestane (25 mg orally once daily) (n = 485) vs. placebo in combination with exemestane (n = 239) was evaluated in a randomized, controlled trial (BOLERO-2) in patients with advanced or metastatic hormone receptor-positive, HER2-negative breast cancer. The median age of patients was 61 years (28 to 93 years), and 75% were white. The median follow-up was approximately 13 months.

The most common adverse reactions (incidence ≥ 30%) were stomatitis, infections, rash, fatigue, diarrhea, and decreased appetite. The most common Grade 3-4 adverse reactions (incidence ≥ 2%) were stomatitis, infections, hyperglycemia, fatigue, dyspnea, pneumonitis, and diarrhea. The most common laboratory abnormalities (incidence ≥ 50%) were hypercholesterolemia, hyperglycemia, increased aspartate transaminase (AST), anemia, leukopenia, thrombocytopenia, lymphopenia, increased alanine transaminase (ALT), and hypertriglyceridemia. The most common Grade 3-4 laboratory abnormalities (incidence ≥ 3%) were lymphopenia, hyperglycemia, anemia, hypokalemia, increased AST, increased ALT, and thrombocytopenia.

Fatal adverse reactions occurred in 2% of patients who received AFINITOR. The rate of adverse reactions resulting in permanent discontinuation was 24% for the AFINITOR arm. Dose adjustments (interruptions or reductions) occurred in 63% of patients in the AFINITOR arm.

Adverse reactions reported with an incidence of ≥ 10% for patients receiving AFINITOR vs. placebo are presented in Table 6. Laboratory abnormalities are presented in Table 7. The median duration of treatment with AFINITOR was 23.9 weeks; 33% were exposed to AFINITOR for a period of ≥ 32 weeks.

Table 6: Adverse Reactions Reported in ≥ 10% of Patients With Hormone Receptor-Positive Breast Cancer in BOLERO-2
 | AFINITOR with Exemestane N = 482 |  | Placebo with Exemestane N = 238
 | All Grades | Grade 3-4 | All Grades | Grade 3-4
 | % | % | % | %
Gastrointestinal
Stomatitisa | 67 | 8d | 11 | 0.8
Diarrhea | 33 | 2 | 18 | 0.8
Nausea | 29 | 0.4 | 28 | 1
Vomiting | 17 | 1 | 12 | 0.8
Constipation | 14 | 0.4d | 13 | 0.4
Dry mouth | 11 | 0 | 7 | 0
General
Fatigue | 36 | 4 | 27 | 1d
Edema peripheral | 19 | 1d | 6 | 0.4d
Pyrexia | 15 | 0.2d | 7 | 0.4d
Asthenia | 13 | 2 | 4 | 0
Infections
Infectionsb | 50 | 6 | 25 | 2d
Investigations
Weight loss | 25 | 1d | 6 | 0
Metabolism and nutrition
Decreased appetite | 30 | 1d | 12 | 0.4d
Hyperglycemia | 14 | 5 | 2 | 0.4d
Musculoskeletal and connective tissue
Arthralgia | 20 | 0.8d | 17 | 0
Back pain | 14 | 0.2d | 10 | 0.8d
Pain in extremity | 9 | 0.4d | 11 | 2d
Nervous system
Dysgeusia | 22 | 0.2d | 6 | 0
Headache | 21 | 0.4d | 14 | 0
Psychiatric
Insomnia | 13 | 0.2d | 8 | 0
Respiratory, thoracic and mediastinal
Cough | 24 | 0.6d | 12 | 0
Dyspnea | 21 | 4 | 11 | 1
Epistaxis | 17 | 0 | 1 | 0
Pneumonitisc | 19 | 4 | 0.4 | 0
Skin and subcutaneous tissue
Rash | 39 | 1d | 6 | 0
Pruritus | 13 | 0.2d | 5 | 0
Alopecia | 10 | 0 | 5 | 0
Vascular
Hot flush | 6 | 0 | 14 | 0
Grading according to NCI CTCAE Version 3.0.
aIncludes stomatitis, mouth ulceration, aphthous stomatitis, glossodynia, gingival pain, glossitis, and lip ulceration.
bIncludes all reported infections, including but not limited to, urinary tract infections, respiratory tract (upper and lower) infections, skin infections, and gastrointestinal tract infections.
cIncludes pneumonitis, interstitial lung disease, lung infiltration, and pulmonary fibrosis.
dNo Grade 4 adverse reactions were reported.

Table 7: Selected Laboratory Abnormalities Reported in ≥ 10% of Patients With Hormone Receptor-Positive Breast Cancer in BOLERO-2
Laboratory Parameter | AFINITOR with Exemestane N = 482 |  | Placebo with Exemestane N = 238
 | All Grades | Grade 3-4 | All Grades | Grade 3-4
 | % | % | % | %
Hematologya
Anemia | 68 | 6 | 40 | 1
Leukopenia | 58 | 2b | 28 | 6
Thrombocytopenia | 54 | 3 | 5 | 0.4
Lymphopenia | 54 | 12 | 37 | 6
Neutropenia | 31 | 2b | 11 | 2
Chemistry
Hypercholesterolemia | 70 | 1 | 38 | 2
Hyperglycemia | 69 | 9 | 44 | 1
Increased AST | 69 | 4 | 45 | 3
Increased ALT | 51 | 4 | 29 | 5b
Hypertriglyceridemia | 50 | 0.8b | 26 | 0
Hypoalbuminemia | 33 | 0.8b | 16 | 0.8b
Hypokalemia | 29 | 4 | 7 | 1b
Increased creatinine | 24 | 2 | 13 | 0
Grading according to NCI CTCAE Version 3.0.
aReflects corresponding adverse drug reaction reports of anemia, leukopenia, lymphopenia, neutropenia, and thrombocytopenia (collectively as pancytopenia), which occurred at lower frequency.
bNo Grade 4 laboratory abnormalities were reported.

Topical Prophylaxis for Stomatitis

In a single arm study (SWISH; N = 92) in postmenopausal women with hormone receptor-positive, HER2-negative breast cancer beginning AFINITOR (10 mg orally once daily) in combination with exemestane (25 mg orally once daily), patients started dexamethasone 0.5 mg/5 mL alcohol-free mouthwash (10 mL swished for 2 minutes and spat, 4 times daily for 8 weeks) concurrently with AFINITOR and exemestane. No food or drink was to be consumed for at least 1 hour after swishing and spitting the dexamethasone mouthwash. The primary objective of this study was to assess the incidence of Grade 2 to 4 stomatitis within 8 weeks. The incidence of Grade 2 to 4 stomatitis within 8 weeks was 2%, which was lower than the 33% reported in the BOLERO-2 trial. The incidence of Grade 1 stomatitis was 19%. No cases of Grade 3 or 4 stomatitis were reported. Oral candidiasis was reported in 2% of patients in this study compared to 0.2% in the BOLERO-2 trial.

Coadministration of AFINITOR/AFINITOR DISPERZ and dexamethasone alcohol-free oral solution has not been studied in pediatric patients.

Pancreatic Neuroendocrine Tumors (PNET)

In a randomized, controlled trial (RADIANT-3) of AFINITOR (n = 204) vs. placebo (n = 203) in patients with advanced PNET the median age of patients was 58 years (20 to 87 years), 79% were white, and 55% were male. Patients on the placebo arm could cross over to open-label AFINITOR upon disease progression.

The most common adverse reactions (incidence ≥ 30%) were stomatitis, rash, diarrhea, fatigue, edema, abdominal pain, nausea, fever, and headache. The most common Grade 3-4 adverse reactions (incidence ≥ 5%) were stomatitis and diarrhea. The most common laboratory abnormalities (incidence ≥ 50%) were anemia, hyperglycemia, increased alkaline phosphatase, hypercholesterolemia, decreased bicarbonate, and increased AST. The most common Grade 3-4 laboratory abnormalities (incidence ≥ 3%) were hyperglycemia, lymphopenia, anemia, hypophosphatemia, increased alkaline phosphatase, neutropenia, increased AST, hypokalemia, and thrombocytopenia.

Deaths during double-blind treatment where an adverse reaction was the primary cause occurred in seven patients on AFINITOR. Causes of death on the AFINITOR arm included one case of each of the following: acute renal failure, acute respiratory distress, cardiac arrest, death (cause unknown), hepatic failure, pneumonia, and sepsis. After cross-over to open-label AFINITOR, there were three additional deaths, one due to hypoglycemia and cardiac arrest in a patient with insulinoma, one due to myocardial infarction with congestive heart failure, and the other due to sudden death. The rate of adverse reactions resulting in permanent discontinuation was 20% for the AFINITOR group. Dose delay or reduction was necessary in 61% of AFINITOR patients. Grade 3-4 renal failure occurred in six patients in the AFINITOR arm. Thrombotic events included five patients with pulmonary embolus in the AFINITOR arm as well as three patients with thrombosis in the AFINITOR arm.

Table 8 compares the incidence of adverse reactions reported with an incidence of ≥ 10% for patients receiving AFINITOR vs. placebo. Laboratory abnormalities are summarized in Table 9. The median duration of treatment in patients who received AFINITOR was 37 weeks.

In female patients aged 18 to 55 years, irregular menstruation occurred in 5 of 46 (11%) AFINITOR-treated females.

Table 8: Adverse Reactions Reported in ≥ 10% of Patients With PNET in RADIANT-3
 | AFINITOR N = 204 |  | Placebo N = 203
 | All Grades | Grade 3-4 | All Grades | Grade 3-4
 | % | % | % | %
Gastrointestinal
Stomatitisa | 70 | 7d | 20 | 0
Diarrheab | 50 | 6 | 25 | 3d
Abdominal pain | 36 | 4d | 32 | 7
Nausea | 32 | 2d | 33 | 2d
Vomiting | 29 | 1d | 21 | 2d
Constipation | 14 | 0 | 13 | 0.5d
Dry mouth | 11 | 0 | 4 | 0
General
Fatigue/malaise | 45 | 4 | 27 | 3
Edema (general and peripheral) | 39 | 2 | 12 | 1d
Fever | 31 | 1 | 13 | 0.5d
Asthenia | 19 | 3d | 20 | 3d
Infections
Nasopharyngitis/rhinitis/URI | 25 | 0 | 13 | 0
Urinary tract infection | 16 | 0 | 6 | 0.5d
Investigations
Weight loss | 28 | 0.5d | 11 | 0
Metabolism and nutrition
Decreased appetite | 30 | 1d | 18 | 1d
Diabetes mellitus | 10 | 2d | 0.5 | 0
Musculoskeletal and connective tissue
Arthralgia | 15 | 1 | 7 | 0.5d
Back pain | 15 | 1d | 11 | 1d
Pain in extremity | 14 | 0.5d | 6 | 1d
Muscle spasms | 10 | 0 | 4 | 0
Nervous system
Headache/migraine | 30 | 0.5d | 15 | 1d
Dysgeusia | 19 | 0 | 5 | 0
Dizziness | 12 | 0.5d | 7 | 0
Psychiatric
Insomnia | 14 | 0 | 8 | 0
Respiratory, thoracic and mediastinal
Cough/productive cough | 25 | 0.5d | 13 | 0
Epistaxis | 22 | 0 | 1 | 0
Dyspnea/dyspnea exertional | 20 | 3 | 7 | 0.5d
Pneumonitisc | 17 | 4 | 0 | 0
Oropharyngeal pain | 11 | 0 | 6 | 0
Skin and subcutaneous
Rash | 59 | 0.5 | 19 | 0
Nail disorders | 22 | 0.5 | 2 | 0
Pruritus/pruritus generalized | 21 | 0 | 13 | 0
Dry skin/xeroderma | 13 | 0 | 6 | 0
Vascular
Hypertension | 13 | 1 | 6 | 1d
Grading according to NCI CTCAE Version 3.0.
aIncludes stomatitis, aphthous stomatitis, gingival pain/swelling/ulceration, glossitis, glossodynia, lip ulceration, mouth ulceration, tongue ulceration, and mucosal inflammation.
bIncludes diarrhea, enteritis, enterocolitis, colitis, defecation urgency, and steatorrhea.
cIncludes pneumonitis, interstitial lung disease, pulmonary fibrosis, and restrictive pulmonary disease.
dNo Grade 4 adverse reactions were reported.

Table 9: Selected Laboratory Abnormalities Reported in ≥ 10% of Patients With PNET in RADIANT-3
Laboratory parameter | AFINITOR N = 204 |  | Placebo N = 203
 | All Grades | Grade 3-4 | All Grades | Grade 3-4
 | % | % | % | %
Hematology
Anemia | 86 | 15 | 63 | 1
Lymphopenia | 45 | 16 | 22 | 4
Thrombocytopenia | 45 | 3 | 11 | 0
Leukopenia | 43 | 2 | 13 | 0
Neutropenia | 30 | 4 | 17 | 2
Chemistry
Hyperglycemia (fasting) | 75 | 17 | 53 | 6
Increased alkaline phosphatase | 74 | 8 | 66 | 8
Hypercholesterolemia | 66 | 0.5 | 22 | 0
Bicarbonate decreased | 56 | 0 | 40 | 0
Increased AST | 56 | 4 | 41 | 4
Increased ALT | 48 | 2 | 35 | 2
Hypophosphatemia | 40 | 10 | 14 | 3
Hypertriglyceridemia | 39 | 0 | 10 | 0
Hypocalcemia | 37 | 0.5 | 12 | 0
Hypokalemia | 23 | 4 | 5 | 0
Increased creatinine | 19 | 2 | 14 | 0
Hyponatremia | 16 | 1 | 16 | 1
Hypoalbuminemia | 13 | 1 | 8 | 0
Hyperbilirubinemia | 10 | 1 | 14 | 2
Hyperkalemia | 7 | 0 | 10 | 0.5
Grading according to NCI CTCAE Version 3.0.

Neuroendocrine Tumors (NET) of Gastrointestinal (GI) or Lung Origin

In a randomized, controlled trial (RADIANT-4) of AFINITOR (n = 202 treated) vs. placebo (n = 98 treated) in patients with advanced non-functional NET of GI or lung origin, the median age of patients was 63 years (22-86 years), 76% were white, and 53% were female. The median duration of exposure to AFINITOR was 9.3 months; 64% of patients were treated for ≥ 6 months and 39% were treated for ≥ 12 months. AFINITOR was discontinued for adverse reactions in 29% of patients, dose reduction or delay was required in 70% of AFINITOR-treated patients.

Serious adverse reactions occurred in 42% of AFINITOR-treated patients and included 3 fatal events (cardiac failure, respiratory failure, and septic shock). Adverse reactions occurring at an incidence of ≥ 10% and at ≥ 5% absolute incidence over placebo (all Grades) or ≥ 2% higher incidence over placebo (Grade 3 and 4) are presented in Table 10. Laboratory abnormalities are presented in Table 11.

Table 10: Adverse Reactions in ≥ 10% of AFINITOR-Treated Patients With Non-Functional NET of GI or Lung Origin in RADIANT-4
 | AFINITOR N = 202 |  | Placebo N = 98
 | All Grades | Grade 3-4 | All Grades | Grade 3-4
 | % | % | % | %
Gastrointestinal
Stomatitisa | 63 | 9d | 22 | 0
Diarrhea | 41 | 9 | 31 | 2d
Nausea | 26 | 3 | 17 | 1d
Vomiting | 15 | 4d | 12 | 2d
General
Peripheral edema | 39 | 3d | 6 | 1d
Fatigue | 37 | 5 | 36 | 1d
Asthenia | 23 | 3 | 8 | 0
Pyrexia | 23 | 2 | 8 | 0
Infections
Infectionsb | 58 | 11 | 29 | 2
Investigations
Weight loss | 22 | 2d | 11 | 1d
Metabolism and nutrition
Decreased appetite | 22 | 1d | 17 | 1d
Nervous system
Dysgeusia | 18 | 1d | 4 | 0
Respiratory, thoracic and mediastinal
Cough | 27 | 0 | 20 | 0
Dyspnea | 20 | 3d | 11 | 2
Pneumonitisc | 16 | 2d | 2 | 0
Epistaxis | 13 | 1d | 3 | 0
Skin and subcutaneous
Rash | 30 | 1d | 9 | 0
Pruritus | 17 | 1d | 9 | 0
Grading according to NCI CTCAE Version 4.03.
aIncludes stomatitis, mouth ulceration, aphthous stomatitis, gingival pain, glossitis, tongue ulceration, and mucosal inflammation.
bUrinary tract infection, nasopharyngitis, upper respiratory tract infection, lower respiratory tract infection (pneumonia, bronchitis), abscess, pyelonephritis, septic shock and viral myocarditis.
cIncludes pneumonitis and interstitial lung disease.
dNo Grade 4 adverse reactions were reported.

Table 11: Selected Laboratory Abnormalities in ≥ 10% of AFINITOR-Treated Patients With Non-Functional NET of GI or Lung Origin in RADIANT-4
 | AFINITOR N = 202 |  | Placebo N = 98
 | All Grades | Grade 3-4 | All Grades | Grade 3-4
 | % | % | % | %
Hematology
Anemia | 81 | 5a | 41 | 2a
Lymphopenia | 66 | 16 | 32 | 2a
Leukopenia | 49 | 2a | 17 | 0
Thrombocytopenia | 33 | 2 | 11 | 0
Neutropenia | 32 | 2a | 15 | 3a
Chemistry
Hypercholesterolemia | 71 | 0 | 37 | 0
Increased AST | 57 | 2 | 34 | 2a
Hyperglycemia (fasting) | 55 | 6a | 36 | 1a
Increased ALT | 46 | 5 | 39 | 1a
Hypophosphatemia | 43 | 4a | 15 | 2a
Hypertriglyceridemia | 30 | 3 | 8 | 1a
Hypokalemia | 27 | 6 | 12 | 3a
Hypoalbuminemia | 18 | 0 | 8 | 0
Grading according to NCI CTCAE Version 4.03.
aNo Grade 4 laboratory abnormalities were reported.

Renal Cell Carcinoma (RCC)

The data described below reflect exposure to AFINITOR (n = 274) and placebo (n = 137) in a randomized, controlled trial (RECORD-1) in patients with metastatic RCC who received prior treatment with sunitinib and/or sorafenib. The median age of patients was 61 years (27 to 85 years), 88% were white, and 78% were male. The median duration of blinded study treatment was 141 days (19 to 451 days) for patients receiving AFINITOR.

The most common adverse reactions (incidence ≥ 30%) were stomatitis, infections, asthenia, fatigue, cough, and diarrhea. The most common Grade 3-4 adverse reactions (incidence ≥ 3%) were infections, dyspnea, fatigue, stomatitis, dehydration, pneumonitis, abdominal pain, and asthenia. The most common laboratory abnormalities (incidence ≥ 50%) were anemia, hypercholesterolemia, hypertriglyceridemia, hyperglycemia, lymphopenia, and increased creatinine. The most common Grade 3-4 laboratory abnormalities (incidence ≥ 3%) were lymphopenia, hyperglycemia, anemia, hypophosphatemia, and hypercholesterolemia.

Deaths due to acute respiratory failure (0.7%), infection (0.7%), and acute renal failure (0.4%) were observed on the AFINITOR arm. The rate of adverse reactions resulting in permanent discontinuation was 14% for the AFINITOR group. The most common adverse reactions leading to treatment discontinuation were pneumonitis and dyspnea. Infections, stomatitis, and pneumonitis were the most common reasons for treatment delay or dose reduction. The most common medical interventions required during AFINITOR treatment were for infections, anemia, and stomatitis.

Adverse reactions reported with an incidence of ≥ 10% for patients receiving AFINITOR vs. placebo are presented in Table 12. Laboratory abnormalities are presented in Table 13.

Table 12: Adverse Reactions Reported in ≥ 10% of Patients With RCC and at a Higher Rate in the AFINITOR Arm than in the Placebo Arm in RECORD-1
 | AFINITOR N = 274 |  | Placebo N = 137
 | All Grades | Grade 3-4 | All Grades | Grade 3-4
 | % | % | % | %
Gastrointestinal
Stomatitisa | 44 | 4 | 8 | 0
Diarrhea | 30 | 2d | 7 | 0
Nausea | 26 | 2d | 19 | 0
Vomiting | 20 | 2d | 12 | 0
Infectionsb | 37 | 10 | 18 | 2
General
Asthenia | 33 | 4 | 23 | 4
Fatigue | 31 | 6d | 27 | 4
Edema peripheral | 25 | < 1d | 8 | < 1d
Pyrexia | 20 | < 1d | 9 | 0
Mucosal inflammation | 19 | 2d | 1 | 0
Respiratory, thoracic and mediastinal
Cough | 30 | < 1d | 16 | 0
Dyspnea | 24 | 8 | 15 | 3d
Epistaxis | 18 | 0 | 0 | 0
Pneumonitisc | 14 | 4d | 0 | 0
Skin and subcutaneous tissue
Rash | 29 | 1d | 7 | 0
Pruritus | 14 | < 1d | 7 | 0
Dry skin | 13 | < 1d | 5 | 0
Metabolism and nutrition
Anorexia | 25 | 2d | 14 | < 1d
Nervous system
Headache | 19 | 1 | 9 | < 1d
Dysgeusia | 10 | 0 | 2 | 0
Musculoskeletal and connective tissue
Pain in extremity | 10 | 1d | 7 | 0
Grading according to NCI CTCAE Version 3.0.
aStomatitis (including aphthous stomatitis), and mouth and tongue ulceration.
bIncludes all reported infections, including but not limited to, respiratory tract (upper and lower) infections, urinary tract infections, and skin infections.
cIncludes pneumonitis, interstitial lung disease, lung infiltration, pulmonary alveolar hemorrhage, pulmonary toxicity, and alveolitis.
dNo Grade 4 adverse reactions were reported.

Other notable adverse reactions occurring more frequently with AFINITOR than with placebo, but with an incidence of < 10% include:

Gastrointestinal: Abdominal pain (9%), dry mouth (8%), hemorrhoids (5%), dysphagia (4%)

General: Weight loss (9%), chest pain (5%), chills (4%), impaired wound healing (< 1%)

Respiratory, thoracic and mediastinal: Pleural effusion (7%), pharyngolaryngeal pain (4%), rhinorrhea (3%)

Skin and subcutaneous tissue: Hand-foot syndrome (reported as palmar-plantar erythrodysesthesia syndrome) (5%), nail disorder (5%), erythema (4%), onychoclasis (4%), skin lesion (4%), acneiform dermatitis (3%), angioedema (< 1%)

Metabolism and nutrition: Exacerbation of pre-existing diabetes mellitus (2%), new onset of diabetes mellitus (< 1%)

Psychiatric: Insomnia (9%)

Nervous system: Dizziness (7%), paresthesia (5%)

Ocular: Eyelid edema (4%), conjunctivitis (2%)

Vascular: Hypertension (4%), deep vein thrombosis (< 1%)

Renal and urinary: Renal failure (3%)

Cardiac: Tachycardia (3%), congestive cardiac failure (1%)

Musculoskeletal and connective tissue: Jaw pain (3%)

Hematologic: Hemorrhage (3%)

Table 13: Selected Laboratory Abnormalities Reported in Patients With RCC at a Higher Rate in the AFINITOR Arm Than the Placebo Arm in RECORD-1
Laboratory parameter | AFINITOR N = 274 |  | Placebo N = 137
 | All Grades | Grade 3-4 | All Grades | Grade 3-4
 | % | % | % | %
Hematologya
Anemia | 92 | 13 | 79 | 6
Lymphopenia | 51 | 18 | 28 | 5b
Thrombocytopenia | 23 | 1b | 2 | < 1
Neutropenia | 14 | < 1 | 4 | 0
Chemistry
Hypercholesterolemia | 77 | 4b | 35 | 0
Hypertriglyceridemia | 73 | < 1b | 34 | 0
Hyperglycemia | 57 | 16 | 25 | 2b
Increased creatinine | 50 | 2b | 34 | 0
Hypophosphatemia | 37 | 6b | 8 | 0
Increased AST | 25 | 1 | 7 | 0
Increased ALT | 21 | 1b | 4 | 0
Hyperbilirubinemia | 3 | 1 | 2 | 0
Grading according to NCI CTCAE Version 3.0.
aReflects corresponding adverse drug reaction reports of anemia, leukopenia, lymphopenia, neutropenia, and thrombocytopenia (collectively pancytopenia), which occurred at lower frequency.
bNo Grade 4 laboratory abnormalities were reported.

Tuberous Sclerosis Complex (TSC)-Associated Renal Angiomyolipoma

The data described below are based on a randomized (2:1), double-blind, placebo-controlled trial (EXIST-2) of AFINITOR in 118 patients with renal angiomyolipoma as a feature of TSC (n = 113) or sporadic lymphangioleiomyomatosis (n = 5). The median age of patients was 31 years (18 to 61 years), 89% were white, and 34% were male. The median duration of blinded study treatment was 48 weeks (2 to 115 weeks) for patients receiving AFINITOR.

The most common adverse reaction reported for AFINITOR (incidence ≥ 30%) was stomatitis. The most common Grade 3-4 adverse reactions (incidence ≥ 2%) were stomatitis and amenorrhea. The most common laboratory abnormalities (incidence ≥ 50%) were hypercholesterolemia, hypertriglyceridemia, and anemia. The most common Grade 3-4 laboratory abnormality (incidence ≥ 3%) was hypophosphatemia.

The rate of adverse reactions resulting in permanent discontinuation was 3.8% in the AFINITOR-treated patients. Adverse reactions leading to permanent discontinuation in the AFINITOR arm were hypersensitivity/angioedema/bronchospasm, convulsion, and hypophosphatemia. Dose adjustments (interruptions or reductions) due to adverse reactions occurred in 52% of AFINITOR-treated patients. The most common adverse reaction leading to AFINITOR dose adjustment was stomatitis.

Adverse reactions reported with an incidence of ≥ 10% for patients receiving AFINITOR and occurring more frequently with AFINITOR than with placebo are presented in Table 14. Laboratory abnormalities are presented in Table 15.

Table 14: Adverse Reactions Reported in ≥ 10% of AFINITOR-Treated Patients With TSC-Associated Renal Angiomyolipoma in EXIST-2
 | AFINITOR N = 79 |  | Placebo N = 39
 | All Grades | Grade 3-4 | All Grades | Grade 3-4
 | % | % | % | %
Gastrointestinal
Stomatitisa | 78 | 6b | 23 | 0
Vomiting | 15 | 0 | 5 | 0
Diarrhea | 14 | 0 | 5 | 0
General
Peripheral edema | 13 | 0 | 8 | 0
Infections
Upper respiratory tract infection | 11 | 0 | 5 | 0
Musculoskeletal and connective tissue
Arthralgia | 13 | 0 | 5 | 0
Respiratory, thoracic and mediastinal
Cough | 20 | 0 | 13 | 0
Skin and subcutaneous tissue
Acne | 22 | 0 | 5 | 0
Grading according to NCI CTCAE Version 3.0.
aIncludes stomatitis, aphthous stomatitis, mouth ulceration, gingival pain, glossitis, and glossodynia.
bNo Grade 4 adverse reactions were reported.

Amenorrhea occurred in 15% of AFINITOR-treated females (8 of 52). Other adverse reactions involving the female reproductive system were menorrhagia (10%), menstrual irregularities (10%), and vaginal hemorrhage (8%).

The following additional adverse reactions occurred in less than 10% of AFINITOR-treated patients: epistaxis (9%), decreased appetite (6%), otitis media (6%), depression (5%), abnormal taste (5%), increased blood luteinizing hormone (LH) levels (4%), increased blood follicle stimulating hormone (FSH) levels (3%), hypersensitivity (3%), ovarian cyst (3%), pneumonitis (1%), and angioedema (1%).

Table 15: Selected Laboratory Abnormalities Reported in AFINITOR-Treated Patients With TSC-Associated Renal Angiomyolipoma in EXIST-2
 | AFINITOR N = 79 |  | Placebo N = 39
 | All Grades | Grade 3-4 | All Grades | Grade 3-4
 | % | % | % | %
Hematology
Anemia | 61 | 0 | 49 | 0
Leukopenia | 37 | 0 | 21 | 0
Neutropenia | 25 | 1 | 26 | 0
Lymphopenia | 20 | 1a | 8 | 0
Thrombocytopenia | 19 | 0 | 3 | 0
Chemistry
Hypercholesterolemia | 85 | 1a | 46 | 0
Hypertriglyceridemia | 52 | 0 | 10 | 0
Hypophosphatemia | 49 | 5a | 15 | 0
Increased alkaline phosphatase | 32 | 1a | 10 | 0
Increased AST | 23 | 1a | 8 | 0
Increased ALT | 20 | 1a | 15 | 0
Hyperglycemia (fasting) | 14 | 0 | 8 | 0
Grading according to NCI CTCAE Version 3.0.
aNo Grade 4 laboratory abnormalities were reported.

Updated safety information from 112 patients treated with AFINITOR for a median duration of 3.9 years identified the following additional adverse reactions and selected laboratory abnormalities: increased partial thromboplastin time (63%), increased prothrombin time (40%), decreased fibrinogen (38%), urinary tract infection (31%), proteinuria (18%), abdominal pain (16%), pruritus (12%), gastroenteritis (12%), myalgia (11%), and pneumonia (10%).

TSC-Associated Subependymal Giant Cell Astrocytoma (SEGA)

The data described below are based on a randomized (2:1), double-blind, placebo-controlled trial (EXIST-1) of AFINITOR in 117 patients with SEGA and TSC. The median age of patients was 9.5 years (0.8 to 26 years), 93% were white, and 57% were male. The median duration of blinded study treatment was 52 weeks (24 to 89 weeks) for patients receiving AFINITOR.

The most common adverse reactions reported for AFINITOR (incidence ≥ 30%) were stomatitis and respiratory tract infection. The most common Grade 3-4 adverse reactions (incidence ≥ 2%) were stomatitis, pyrexia, pneumonia, gastroenteritis, aggression, agitation, and amenorrhea. The most common laboratory abnormalities (incidence ≥ 50%) were hypercholesterolemia and elevated partial thromboplastin time. The most common Grade 3-4 laboratory abnormality (incidence ≥ 3%) was neutropenia.

There were no adverse reactions resulting in permanent discontinuation. Dose adjustments (interruptions or reductions) due to adverse reactions occurred in 55% of AFINITOR-treated patients. The most common adverse reaction leading to AFINITOR dose adjustment was stomatitis.

Adverse reactions reported with an incidence of ≥ 10% for patients receiving AFINITOR and occurring more frequently with AFINITOR than with placebo are reported in Table 16. Laboratory abnormalities are presented in Table 17.

Table 16: Adverse Reactions Reported in ≥ 10% of AFINITOR-Treated Patients With TSC-Associated SEGA in EXIST-1
 | AFINITOR N = 78 |  | Placebo N = 39
 | All Grades | Grade 3-4 | All Grades | Grade 3-4
 | % | % | % | %
Gastrointestinal
Stomatitisa | 62 | 9f | 26 | 3f
Vomiting | 22 | 1f | 13 | 0
Diarrhea | 17 | 0 | 5 | 0
Constipation | 10 | 0 | 3 | 0
Infections
Respiratory tract infectionb | 31 | 3 | 23 | 0
Gastroenteritisc | 10 | 5 | 3 | 0
Pharyngitis streptococcal | 10 | 0 | 3 | 0
General
Pyrexia | 23 | 6f | 18 | 3f
Fatigue | 14 | 0 | 3 | 0
Psychiatric
Anxiety, aggression or other behavioral disturbanced | 21 | 5f | 3 | 0
Skin and subcutaneous tissue
Rashe | 21 | 0 | 8 | 0
Acne | 10 | 0 | 5 | 0
Grading according to NCI CTCAE Version 3.0.
aIncludes mouth ulceration, stomatitis, and lip ulceration.
bIncludes respiratory tract infection, upper respiratory tract infection, and respiratory tract infection viral.
cIncludes gastroenteritis, gastroenteritis viral, and gastrointestinal infection.
dIncludes agitation, anxiety, panic attack, aggression, abnormal behavior, and obsessive compulsive disorder.
eIncludes rash, rash generalized, rash macular, rash maculo-papular, rash papular, dermatitis allergic, and urticaria.
fNo Grade 4 adverse reactions were reported.

Amenorrhea occurred in 17% of AFINITOR-treated females aged 10 to 55 years (3 of 18). For this same group of AFINITOR-treated females, the following menstrual abnormalities were reported: dysmenorrhea (6%), menorrhagia (6%), metrorrhagia (6%), and unspecified menstrual irregularity (6%).

The following additional adverse reactions occurred in less than 10% of AFINITOR-treated patients: nausea (8%), pain in extremity (8%), insomnia (6%), pneumonia (6%), epistaxis (5%), hypersensitivity (3%), increased blood luteinizing hormone (LH) levels (1%), and pneumonitis (1%).

Table 17: Selected Laboratory Abnormalities Reported in AFINITOR-Treated Patients With TSC-Associated SEGA in EXIST-1
 | AFINITOR N = 78 |  | Placebo N = 39
 | All Grades | Grade 3-4 | All Grades | Grade 3-4
 | % | % | % | %
Hematology
Elevated partial thromboplastin time | 72 | 3a | 44 | 5a
Neutropenia | 46 | 9a | 41 | 3a
Anemia | 41 | 0 | 21 | 0
Chemistry
Hypercholesterolemia | 81 | 0 | 39 | 0
Elevated AST | 33 | 0 | 0 | 0
Hypertriglyceridemia | 27 | 0 | 15 | 0
Elevated ALT | 18 | 0 | 3 | 0
Hypophosphatemia | 9 | 1a | 3 | 0
Grading according to NCI CTCAE Version 3.0.
aNo Grade 4 laboratory abnormalities were reported.

Updated safety information from 111 patients treated with AFINITOR for a median duration of 47 months identified the following additional notable adverse reactions and selected laboratory abnormalities: decreased appetite (14%), hyperglycemia (13%), hypertension (11%), urinary tract infection (9%), decreased fibrinogen (8%), cellulitis (6%), abdominal pain (5%), decreased weight (5%), elevated creatinine (5%), and azoospermia (1%).

TSC-Associated Partial-Onset Seizures

The data described below are based on the 18-week Core phase of a randomized, double-blind, multicenter, three-arm trial (EXIST-3) comparing two everolimus trough levels (3-7 ng/mL and 9-15 ng/mL) to placebo as adjunctive antiepileptic therapy in patients with TSC-associated partial-onset seizures. A total of 366 patients were randomized to AFINITOR DISPERZ low trough (LT) (n = 117), AFINITOR DISPERZ high trough (HT) (n = 130), or placebo (n = 119). The median age of patients was 10 years (2.2 to 56 years; 28% were < 6 years, 31% were 6 to < 12 years, 22% were 12 to < 18 years, and 18% were ≥ 18 years), 65% were white, and 52% were male. Patients received between one and three concomitant antiepileptic drugs.

The most common adverse reaction reported for AFINITOR DISPERZ in both arms (incidence ≥ 30%) was stomatitis. The most common Grade 3-4 adverse reactions (incidence ≥ 2%) were stomatitis, pneumonia, and irregular menstruation. The most common laboratory abnormality (incidence ≥ 50%) was hypercholesterolemia. The most common Grade 3-4 laboratory abnormality (incidence ≥ 2%) was neutropenia.

Adverse reactions leading to study drug discontinuation occurred in 5% and 3% of patients in the LT and HT arms, respectively. The most common adverse reaction (incidence ≥ 1%) leading to discontinuation was stomatitis. Dose adjustments (interruptions or reductions) due to adverse reactions occurred in 24% and 35% of patients in the LT and HT arms, respectively. The most common adverse reactions (incidence ≥ 3%) leading to dose adjustments in the AFINITOR DISPERZ arms were stomatitis, pneumonia, and pyrexia.

Adverse reactions reported with an incidence of ≥ 10% for patients receiving AFINITOR DISPERZ are presented in Table 18. Laboratory abnormalities are presented in Table 19.

Table 18: Adverse Reactions Reported in ≥ 10% of AFINITOR DISPERZ-Treated Patients With TSC-Associated Partial-Onset Seizures in EXIST-3
 | AFINITOR DISPERZ |  |  |  | Placebo
 | Target of 3-7 ng/mL N = 117 |  | Target of 9-15 ng/mL N = 130 |  | N = 119
 | All Grades % | Grade 3-4 % | All Grades % | Grade 3-4 % | All Grades % | Grade 3-4 %
Gastrointestinal
Stomatitisa | 55 | 3b | 64 | 4b | 9 | 0
Diarrhea | 17 | 0 | 22 | 0 | 5 | 0
Vomiting | 12 | 0 | 10 | 2b | 9 | 0
Infections
Nasopharyngitis | 14 | 0 | 16 | 0 | 16 | 0
Upper respiratory tract infection | 13 | 0 | 15 | 0 | 13 | 0.8b
General
Pyrexia | 20 | 0 | 14 | 0.8b | 5 | 0
Respiratory, thoracic and mediastinal
Cough | 11 | 0 | 10 | 0 | 3 | 0
Skin and subcutaneous tissue
Rash | 6 | 0 | 10 | 0 | 3 | 0
Grading according to NCI CTCAE Version 4.03.
aIncludes stomatitis, mouth ulceration, aphthous ulcer, lip ulceration, tongue ulceration, mucosal inflammation, gingival pain.
bNo Grade 4 adverse reactions were reported.

The following additional adverse reactions occurred in < 10% of AFINITOR DISPERZ treated patients (% AFINITOR DISPERZ LT, % AFINITOR DISPERZ HT): decreased appetite (9%, 7%), pneumonia (2%, 4%), aggression (2%, 0.8%), proteinuria (0%, 2%), menorrhagia (0.9%, 0.8%), and pneumonitis (0%, 0.8%).

Table 19: Selected Laboratory Abnormalities Reported in ≥ 10% AFINITOR DISPERZ-Treated Patients With TSC-Associated Partial-Onset Seizures
 | AFINITOR DISPERZ |  |  |  | Placebo
 | Target of 3-7 ng/mL N = 117 |  | Target of 9-15 ng/mL N = 130 |  | N = 119
 | All Grades % | Grade 3-4 % | All Grades % | Grade 3-4 % | All Grades % | Grade 3-4 %
Hematology
Neutropenia | 25 | 4a | 37 | 6 | 23 | 7a
Anemia | 27 | 0.9a | 30 | 0 | 21 | 0.8a
Thrombocytopenia | 12 | 0 | 15 | 0 | 6 | 0
Chemistry
Hypercholesterolemia | 86 | 0 | 85 | 0.8a | 58 | 0
Hypertriglyceridemia | 43 | 2a | 39 | 2 | 22 | 0
Increased ALT | 17 | 0 | 22 | 0 | 6 | 0
Increased AST | 13 | 0 | 19 | 0 | 4 | 0
Hyperglycemia | 19 | 0 | 18 | 0 | 17 | 0
Increased alkaline phosphatase | 24 | 0 | 16 | 0 | 29 | 0
Hypophosphatemia | 9 | 0.9a | 16 | 2 | 3 | 0
Grading according to NCI CTCAE version 4.03.
aNo Grade 4 laboratory abnormalities were reported.

Updated safety information from 357 patients treated with AFINITOR DISPERZ for a median duration of 48 weeks identified the following additional notable adverse reactions: hypersensitivity (0.6%), angioedema (0.3%), and ovarian cyst (0.3%).

6.2 Postmarketing Experience

The following adverse reactions have been identified during postapproval use of AFINITOR/AFINITOR DISPERZ. Because these reactions are reported voluntarily from a population of uncertain size, it is not always possible to reliably estimate frequency or establish a causal relationship to drug exposure:

- Blood and lymphatic disorders: Thrombotic microangiopathy
- Cardiac: Cardiac failure with some cases reported with pulmonary hypertension (including pulmonary arterial hypertension) as a secondary event
- Gastrointestinal: Acute pancreatitis
- Hepatobiliary: Cholecystitis and cholelithiasis
- Infections: Sepsis and septic shock
- Nervous system: Reflex sympathetic dystrophy
- Vascular: Arterial thrombotic events, lymphedema
- Injury, poisoning and procedural complications: Radiation Sensitization and Radiation Recall

7 DRUG INTERACTIONS

7.1 Effect of Other Drugs on AFINITOR/AFINITOR DISPERZ

Inhibitors

Avoid the concomitant use of P-gp and strong CYP3A4 inhibitors [see Dosage and Administration (2.11), Clinical Pharmacology (12.3)].

Reduce the dose for patients taking AFINITOR/AFINITOR DISPERZ with a P-gp and moderate CYP3A4 inhibitor as recommended [see Dosage and Administration (2.11), Clinical Pharmacology (12.3)].

Inducers

Increase the dose for patients taking AFINITOR/AFINITOR DISPERZ with a P-gp and strong CYP3A4 inducer as recommended [see Dosage and Administration (2.12), Clinical Pharmacology (12.3)].

7.2 Effects of Combination Use of Angiotensin Converting Enzyme (ACE) Inhibitors

Patients taking concomitant ACE inhibitors with AFINITOR/AFINITOR DISPERZ may be at increased risk for angioedema. Avoid the concomitant use of ACE inhibitors with AFINITOR/AFINITOR DISPERZ [see Warnings and Precautions (5.4)].

8 USE IN SPECIFIC POPULATIONS

8.1 Pregnancy

Risk Summary

Based on animal studies and the mechanism of action [see Clinical Pharmacology (12.1)], AFINITOR/AFINITOR DISPERZ can cause fetal harm when administered to a pregnant woman. There are limited case reports of AFINITOR use in pregnant women; however, these reports are not sufficient to inform about risks of birth defects or miscarriage. In animal studies, everolimus caused embryo-fetal toxicities in rats when administered during the period of organogenesis at maternal exposures that were lower than human exposures at the recommended dose of AFINITOR 10 mg orally once daily (see Data). Advise pregnant women of the potential risk to the fetus.

In the U.S. general population, the estimated background risk of major birth defects and miscarriage is 2% to 4% and 15% to 20% of clinically recognized pregnancies, respectively.

Data

Animal Data

In animal reproductive studies, oral administration of everolimus to female rats before mating and through organogenesis induced embryo-fetal toxicities, including increased resorption, pre-implantation and post-implantation loss, decreased numbers of live fetuses, malformation (e.g., sternal cleft), and retarded skeletal development. These effects occurred in the absence of maternal toxicities. Embryo-fetal toxicities in rats occurred at doses ≥ 0.1 mg/kg (0.6 mg/m^2) with resulting exposures of approximately 4% of the human exposure at the recommended dose of AFINITOR 10 mg orally once daily based on area under the curve (AUC). In rabbits, embryo-toxicity evident as an increase in resorptions occurred at an oral dose of 0.8 mg/kg (9.6 mg/m^2), approximately 1.6 times the recommended dose of AFINITOR 10 mg orally once daily or the median dose administered to patients with tuberous sclerosis complex (TSC)-associated subependymal giant cell astrocytoma (SEGA), and 1.3 times the median dose administered to patients with TSC-associated partial-onset seizures based on BSA. The effect in rabbits occurred in the presence of maternal toxicities.

In a pre- and post-natal development study in rats, animals were dosed from implantation through lactation. At the dose of 0.1 mg/kg (0.6 mg/m^2), there were no adverse effects on delivery and lactation or signs of maternal toxicity; however, there were reductions in body weight (up to 9% reduction from the control) and in survival of offspring (~5% died or missing). There were no drug-related effects on the developmental parameters (morphological development, motor activity, learning, or fertility assessment) in the offspring.

8.2 Lactation

Risk Summary

There are no data on the presence of everolimus or its metabolites in human milk, the effects of everolimus on the breastfed infant or on milk production. Everolimus and its metabolites passed into the milk of lactating rats at a concentration 3.5 times higher than in maternal serum. Because of the potential for serious adverse reactions in breastfed infants from everolimus, advise women not to breastfeed during treatment with AFINITOR/AFINITOR DISPERZ and for 2 weeks after the last dose.

8.3 Females and Males of Reproductive Potential

Pregnancy Testing

Verify the pregnancy status of females of reproductive potential prior to starting AFINITOR/AFINITOR DISPERZ [see Use in Specific Populations (8.1)].

Contraception

AFINITOR/AFINITOR DISPERZ can cause fetal harm when administered to pregnant women [see Use in Specific Populations (8.1)].

Females: Advise female patients of reproductive potential to use effective contraception during treatment with AFINITOR/AFINITOR DISPERZ and for 8 weeks after the last dose.

Males: Advise male patients with female partners of reproductive potential to use effective contraception during treatment with AFINITOR/AFINITOR DISPERZ and for 4 weeks after the last dose.

Infertility

Females: Menstrual irregularities, secondary amenorrhea, and increases in luteinizing hormone (LH) and follicle stimulating hormone (FSH) occurred in female patients taking AFINITOR/AFINITOR DISPERZ. Based on these findings, AFINITOR/AFINITOR DISPERZ may impair fertility in female patients [see Adverse Reactions (6.1), Nonclinical Toxicology (13.1)].

Males: Cases of reversible azoospermia have been reported in male patients taking AFINITOR. In male rats, sperm motility, sperm count, plasma testosterone levels and fertility were diminished at AUC similar to those of the clinical dose of AFINITOR 10 mg orally once daily. Based on these findings, AFINITOR/AFINITOR DISPERZ may impair fertility in male patients [see Nonclinical Toxicology (13.1)].

8.4 Pediatric Use

TSC-Associated SEGA

The safety and effectiveness of AFINITOR/AFINITOR DISPERZ have been established in pediatric patients age 1 year and older with TSC-associated SEGA that requires therapeutic intervention but cannot be curatively resected. Use of AFINITOR/AFINITOR DISPERZ for this indication is supported by evidence from a randomized, double-blind, placebo-controlled trial in adult and pediatric patients (EXIST-1); an open-label, single-arm trial in adult and pediatric patients (Study 2485); and additional pharmacokinetic data in pediatric patients [see Adverse Reactions (6.1), Clinical Pharmacology (12.3), Clinical Studies (14.5)]. The safety and effectiveness of AFINITOR/AFINITOR DISPERZ have not been established in pediatric patients less than 1 year of age with TSC-associated SEGA.

In EXIST-1, the incidence of infections and serious infections were reported at a higher frequency in patients < 6 years of age. Ninety-six percent of 23 AFINITOR-treated patients < 6 years had at least one infection compared to 67% of 55 AFINITOR-treated patients ≥ 6 years. Thirty-five percent of 23 AFINITOR-treated patients < 6 years of age had at least 1 serious infection compared to 7% of 55 AFINITOR-treated patients ≥ 6 years.

Although a conclusive determination cannot be made due to the limited number of patients and lack of a comparator arm in the open label follow-up periods of EXIST-1 and Study 2485, AFINITOR did not appear to adversely impact growth and pubertal development in the 115 pediatric patients treated with AFINITOR for a median duration of 4.1 years.

TSC-Associated Partial-Onset Seizures

The safety and effectiveness of AFINITOR DISPERZ has been established for the adjunctive treatment of pediatric patients aged 2 years and older with TSC-associated partial-onset seizures. Use of AFINITOR DISPERZ for this indication is supported by evidence from a randomized, double-blind, placebo-controlled trial in adult and pediatric patients (EXIST-3) with additional pharmacokinetic data in pediatric patients [see Adverse Reactions (6.1), Clinical Pharmacology (12.3), Clinical Studies (14.6)]. The safety and effectiveness of AFINITOR DISPERZ and AFINITOR have not been established for the adjunctive treatment of pediatric patients less than 2 years of age with TSC-associated partial-onset seizures.

The incidence of infections and serious infections were reported at a higher frequency in patients < 6 years of age compared to patients ≥ 6 years old. Seventy-seven percent of 70 AFINITOR DISPERZ-treated patients < 6 years had at least one infection, compared to 53% of 177 AFINITOR DISPERZ-treated patients ≥ 6 years. Sixteen percent of 70 AFINITOR DISPERZ-treated patients < 6 years of age had at least 1 serious infection, compared to 4% of 177 AFINITOR DISPERZ-treated patients ≥ 6 years of age. Two fatal cases due to infections were reported in pediatric patients.

Other Indications

The safety and effectiveness of AFINITOR/AFINITOR DISPERZ in pediatric patients have not been established in:

- Hormone receptor-positive, HER2-negative breast cancer
- Neuroendocrine tumors (NET)
- Renal cell carcinoma (RCC)
- TSC-associated renal angiomyolipoma

8.5 Geriatric Use

In BOLERO-2, 40% of patients with breast cancer treated with AFINITOR were ≥ 65 years of age, while 15% were ≥ 75 years of age. No overall differences in effectiveness were observed between elderly and younger patients. The incidence of deaths due to any cause within 28 days of the last AFINITOR dose was 6% in patients ≥ 65 years of age compared to 2% in patients < 65 years of age. Adverse reactions leading to permanent treatment discontinuation occurred in 33% of patients ≥ 65 years of age compared to 17% in patients < 65 years of age.

In RECORD-1, 41% of patients with renal cell carcinoma treated with AFINITOR were ≥ 65 years of age, while 7% were ≥ 75 years of age. In RADIANT-3, 30% of patients with PNET treated with AFINITOR were ≥ 65 years of age, while 7% were ≥ 75 years of age. No overall differences in safety or effectiveness were observed between elderly and younger patients.

8.6 Hepatic Impairment

AFINITOR/AFINITOR DISPERZ exposure may increase in patients with hepatic impairment [see Clinical Pharmacology (12.3)].

For patients with breast cancer, NET, RCC, and TSC-associated renal angiomyolipoma who have hepatic impairment, reduce the AFINITOR dose as recommended [see Dosage and Administration (2.10)].

For patients with TSC-associated SEGA and TSC-associated partial-onset seizures who have severe hepatic impairment (Child-Pugh class C), reduce the starting dose of AFINITOR/AFINITOR DISPERZ as recommended and adjust the dose based on everolimus trough concentrations [see Dosage and Administration (2.8, 2.10)].

11 DESCRIPTION

AFINITOR (everolimus) and AFINITOR DISPERZ (everolimus tablets for oral suspension) are kinase inhibitors.

The chemical name of everolimus is (1R,9S,12S,15R,16E,18R,19R,21R,23S,24E,26E,28E,30S,32S,35R)-1,18- dihydroxy-12-{(1R)-2-[(1S,3R,4R)-4-(2-hydroxyethoxy)-3-methoxycyclohexyl]-1-methylethyl}-19,30-dimethoxy-15,17,21,23,29,35-hexamethyl-11,36-dioxa-4-aza-tricyclo[30.3.1.0^4,9]hexatriaconta-16,24,26,28-tetraene-2,3,10,14,20-pentaone. The molecular formula is C53H83NO14 and the molecular weight is 958.2 g/mol. The structural formula is:

AFINITOR for oral administration contains 2.5 mg, 5 mg, 7.5 mg, or 10 mg of everolimus and the following inactive ingredients: anhydrous lactose, butylated hydroxytoluene, crospovidone, hypromellose, lactose monohydrate, and magnesium stearate.

AFINITOR DISPERZ for oral administration contains 2 mg, 3 mg, or 5 mg of everolimus and the following inactive ingredients: butylated hydroxytoluene, colloidal silicon dioxide, crospovidone, hypromellose, lactose monohydrate, magnesium stearate, mannitol, and microcrystalline cellulose.

12 CLINICAL PHARMACOLOGY

12.1 Mechanism of Action

Everolimus is an inhibitor of mammalian target of rapamycin (mTOR), a serine-threonine kinase, downstream of the PI3K/AKT pathway. The mTOR pathway is dysregulated in several human cancers and in tuberous sclerosis complex (TSC). Everolimus binds to an intracellular protein, FKBP-12, resulting in an inhibitory complex formation with mTOR complex 1 (mTORC1) and thus inhibition of mTOR kinase activity. Everolimus reduced the activity of S6 ribosomal protein kinase (S6K1) and eukaryotic initiation factor 4E-binding protein (4E-BP1), downstream effectors of mTOR, involved in protein synthesis. S6K1 is a substrate of mTORC1 and phosphorylates the activation domain 1 of the estrogen receptor which results in ligand-independent activation of the receptor. In addition, everolimus inhibited the expression of hypoxia-inducible factor (e.g., HIF-1) and reduced the expression of vascular endothelial growth factor (VEGF). Inhibition of mTOR by everolimus has been shown to reduce cell proliferation, angiogenesis, and glucose uptake in in vitro and/or in vivo studies.

Constitutive activation of the PI3K/Akt/mTOR pathway can contribute to endocrine resistance in breast cancer. In vitro studies show that estrogen-dependent and HER2+ breast cancer cells are sensitive to the inhibitory effects of everolimus, and that combination treatment with everolimus and Akt, HER2, or aromatase inhibitors enhances the anti-tumor activity of everolimus in a synergistic manner.

Two regulators of mTORC1 signaling are the oncogene suppressors tuberin-sclerosis complexes 1 and 2 (TSC1, TSC2). Loss or inactivation of either TSC1 or TSC2 leads to activation of downstream signaling. In TSC, a genetic disorder, inactivating mutations in either the TSC1 or the TSC2 gene lead to hamartoma formation throughout the body as well as seizures and epileptogenesis. Overactivation of mTOR results in neuronal dysplasia, aberrant axonogenesis and dendrite formation, increased excitatory synaptic currents, reduced myelination, and disruption of the cortical laminar structure causing abnormalities in neuronal development and function. Treatment with an mTOR inhibitor in animal models of mTOR dysregulation in the brain resulted in seizure suppression, prevention of the development of new-onset seizures, and prevention of premature death.

12.2 Pharmacodynamics

Exposure-Response Relationship

In patients with TSC-associated subependymal giant cell astrocytoma (SEGA), the magnitude of the reduction in SEGA volume was correlated with the everolimus trough concentration.

In patients with TSC-associated partial-onset seizures, the magnitude of the reduction in absolute seizure frequency was correlated with the everolimus trough concentration.

Cardiac Electrophysiology

In a randomized, placebo-controlled, cross-over study, 59 healthy subjects were administered a single oral dose of AFINITOR (20 mg and 50 mg) and placebo. AFINITOR at single doses up to 50 mg did not prolong the QT/QTc interval.

12.3 Pharmacokinetics

Absorption

After administration of AFINITOR in patients with advanced solid tumors, peak everolimus concentrations are reached 1 to 2 hours after administration of oral doses ranging from 5 mg to 70 mg. Following single doses, Cmax is dose-proportional with daily dosing between 5 mg and 10 mg. With single doses of 20 mg and higher, the increase in Cmax is less than dose-proportional; however, AUC shows dose-proportionality over the 5 mg to 70 mg dose range. Steady-state was achieved within 2 weeks following once-daily dosing.

In patients with TSC-associated SEGA, everolimus Cmin was approximately dose-proportional within the dose range from 1.35 mg/m^2 to 14.4 mg/m^2.

Effect of Food: In healthy subjects, a high-fat meal (containing approximately 1000 calories and 55 grams of fat) reduced systemic exposure to AFINITOR 10 mg (as measured by AUC) by 22% and the peak blood concentration Cmax by 54%. Light-fat meals (containing approximately 500 calories and 20 grams of fat) reduced AUC by 32% and Cmax by 42%.

In healthy subjects who received 9 mg of AFINITOR DISPERZ, high-fat meals (containing approximately 1000 calories and 55 grams of fat) reduced everolimus AUC by 12% and Cmax by 60% and low-fat meals (containing approximately 500 calories and 20 grams of fat) reduced everolimus AUC by 30% and Cmax by 50%.

Relative Bioavailability: The AUCinf of everolimus was equivalent between AFINITOR DISPERZ and AFINITOR; the Cmax of everolimus in the AFINITOR DISPERZ dosage form was 20% to 36% lower than that of AFINITOR. The predicted trough concentrations at steady-state were similar after daily administration.

Distribution

The blood-to-plasma ratio of everolimus, which is concentration-dependent over the range of 5 to 5000 ng/mL, is 17% to 73%. The amount of everolimus confined to the plasma is approximately 20% at blood concentrations observed in cancer patients given AFINITOR 10 mg orally once daily. Plasma protein binding is approximately 74% both in healthy subjects and in patients with moderate hepatic impairment.

Elimination

The mean elimination half-life of everolimus is approximately 30 hours.

Metabolism: Everolimus is a substrate of CYP3A4. Following oral administration, everolimus is the main circulating component in human blood. Six main metabolites of everolimus have been detected in human blood, including three monohydroxylated metabolites, two hydrolytic ring-opened products, and a phosphatidylcholine conjugate of everolimus. These metabolites were also identified in animal species used in toxicity studies, and showed approximately 100-times less activity than everolimus itself.

Excretion: No specific elimination studies have been undertaken in cancer patients. Following the administration of a 3 mg single dose of radiolabeled everolimus in patients who were receiving cyclosporine, 80% of the radioactivity was recovered from the feces, while 5% was excreted in the urine. The parent substance was not detected in urine or feces.

Specific Populations

No relationship was apparent between oral clearance and age or sex in patients with cancer.

Patients with Renal Impairment: No significant influence of creatinine clearance (25 to 178 mL/min) was detected on oral clearance (CL/F) of everolimus.

Patients with Hepatic Impairment: Compared to normal subjects, there was a 1.8-fold, 3.2-fold, and 3.6-fold increase in AUC for subjects with mild (Child-Pugh class A), moderate (Child-Pugh class B), and severe (Child-Pugh class C) hepatic impairment, respectively. In another study, the average AUC of everolimus in subjects with moderate hepatic impairment (Child-Pugh class B) was twice that found in subjects with normal hepatic function [see Dosage and Administration (2.10), Use in Specific Populations (8.6)].

Pediatric Patients: In patients with TSC-associated SEGA or TSC-associated partial-onset seizures, the mean Cmin values normalized to mg/m^2 dose in pediatric patients (< 18 years of age) were lower than those observed in adults, suggesting that everolimus clearance adjusted to BSA was higher in pediatric patients as compared to adults.

Race or Ethnicity: Based on a cross-study comparison, Japanese patients had on average exposures that were higher than non-Japanese patients receiving the same dose. Oral clearance (CL/F) is on average 20% higher in black patients than in white patients.

Drug Interaction Studies

Effect of CYP3A4 and P-glycoprotein (P-gp) Inhibitors on Everolimus: Everolimus exposure increased when AFINITOR was coadministered with:

- ketoconazole (a P-gp and strong CYP3A4 inhibitor) - Cmax and AUC increased by 3.9- and 15-fold, respectively.
- erythromycin (a P-gp and moderate CYP3A4 inhibitor) - Cmax and AUC increased by 2- and 4.4-fold, respectively.
- verapamil (a P-gp and moderate CYP3A4 inhibitor) - Cmax and AUC increased by 2.3- and 3.5-fold, respectively.

Effect of CYP3A4 and P-gp Inducers on Everolimus: The coadministration of AFINITOR with rifampin, a P-gp and strong inducer of CYP3A4, decreased everolimus AUC by 63% and Cmax by 58% compared to AFINITOR alone [see Dosage and Administration (2.12)].

Effect of Everolimus on CYP3A4 Substrates: No clinically significant pharmacokinetic interactions were observed between AFINITOR and the HMG-CoA reductase inhibitors atorvastatin (a CYP3A4 substrate), pravastatin (a non-CYP3A4 substrate), and simvastatin (a CYP3A4 substrate).

The coadministration of an oral dose of midazolam (sensitive CYP3A4 substrate) with AFINITOR resulted in a 25% increase in midazolam Cmax and a 30% increase in midazolam AUC0-inf.

The coadministration of AFINITOR with exemestane increased exemestane Cmin by 45% and C2h by 64%; however, the corresponding estradiol levels at steady state (4 weeks) were not different between the 2 treatment arms. No increase in adverse reactions related to exemestane was observed in patients with hormone receptor-positive, HER2-negative advanced breast cancer receiving the combination.

The coadministration of AFINITOR with long-acting octreotide increased octreotide Cmin by approximately 50%.

Effect of Everolimus on Antiepileptic Drugs (AEDs): Everolimus increased pre-dose concentrations of the carbamazepine, clobazam, oxcarbazepine, and clobazam’s metabolite N-desmethylclobazam by about 10%. Everolimus had no impact on pre-dose concentrations of AEDs that are substrates of CYP3A4 (e.g., clonazepam and zonisamide) or other AEDs, including valproic acid, topiramate, phenobarbital, and phenytoin.

13 NONCLINICAL TOXICOLOGY

13.1 Carcinogenesis, Mutagenesis, Impairment of Fertility

Administration of everolimus for up to 2 years did not indicate oncogenic potential in mice and rats up to the highest doses tested (0.9 mg/kg) corresponding, respectively to 3.9 and 0.2 times the estimated human exposure based on AUC at the recommended dose of AFINITOR 10 mg orally once daily.

Everolimus was not genotoxic in a battery of in vitro assays (Ames mutation test in Salmonella, mutation test in L5178Y mouse lymphoma cells, and chromosome aberration assay in V79 Chinese hamster cells). Everolimus was not genotoxic in an in vivo mouse bone marrow micronucleus test at doses up to 500 mg/kg/day (1500 mg/m^2/day, approximately 255-fold the recommended dose of AFINITOR 10 mg orally once daily, and approximately 200-fold the median dose administered to patients with TSC-associated SEGA and TSC-associated partial-onset seizures, based on the BSA), administered as 2 doses, 24 hours apart.

Based on non-clinical findings, AFINITOR/AFINITOR DISPERZ may impair male fertility. In a 13-week male fertility study in rats, testicular morphology was affected at doses of 0.5 mg/kg and above. Sperm motility, sperm count, and plasma testosterone levels were diminished in rats treated with 5 mg/kg. The exposures at these doses (52 ng•hr/mL and 414 ng•hr/mL, respectively) were within the range of human exposure at the recommended dose of AFINITOR 10 mg orally once daily (560 ng•hr/mL) and resulted in infertility in the rats at 5 mg/kg. Effects on male fertility occurred at AUC0-24h values 10% to 81% lower than human exposure at the recommended dose of AFINITOR 10 mg orally once daily. After a 10-13 week non-treatment period, the fertility index increased from zero (infertility) to 60%.

Oral doses of everolimus in female rats at doses ≥ 0.1 mg/kg (approximately 4% the human exposure based on AUC at the recommended dose of AFINITOR 10 mg orally once daily) resulted in increased incidence of pre-implantation loss, suggesting that the drug may reduce female fertility.

13.2 Animal Toxicology and/or Pharmacology

In juvenile rat toxicity studies, dose-related delayed attainment of developmental landmarks, including delayed eye-opening, delayed reproductive development in males and females and increased latency time during the learning and memory phases were observed at doses as low as 0.15 mg/kg/day.

14 CLINICAL STUDIES

14.1 Hormone Receptor-Positive, HER2-Negative Breast Cancer

A randomized, double-blind, multicenter study (BOLERO-2, NCT00863655) of AFINITOR in combination with exemestane vs. placebo in combination with exemestane was conducted in 724 postmenopausal women with estrogen receptor-positive, HER2-negative advanced breast cancer with recurrence or progression following prior therapy with letrozole or anastrozole. Randomization was stratified by documented sensitivity to prior hormonal therapy (yes vs. no) and by the presence of visceral metastasis (yes vs. no). Sensitivity to prior hormonal therapy was defined as either (1) documented clinical benefit (complete response [CR], partial response [PR], stable disease ≥ 24 weeks) to at least one prior hormonal therapy in the advanced setting or (2) at least 24 months of adjuvant hormonal therapy prior to recurrence. Patients were permitted to have received 0-1 prior lines of chemotherapy for advanced disease. The major efficacy outcome measure was progression-free survival (PFS) evaluated by RECIST (Response Evaluation Criteria in Solid Tumors), based on investigator (local radiology) assessment. Other outcome measures included overall survival (OS) and objective response rate (ORR).

Patients were randomized 2:1 to AFINITOR 10 mg orally once daily in combination with exemestane 25 mg once daily (n = 485) or to placebo in combination with exemestane 25 mg orally once daily (n = 239). The two treatment groups were generally balanced with respect to baseline demographics and disease characteristics. Patients were not permitted to cross over to AFINITOR at the time of disease progression.

The trial demonstrated a statistically significant improvement in PFS by investigator assessment (Table 20 and Figure 1). The results of the PFS analysis based on independent central radiological assessment were consistent with the investigator assessment. PFS results were also consistent across the subgroups of age, race, presence and extent of visceral metastases, and sensitivity to prior hormonal therapy.

ORR was higher in the AFINITOR in combination with exemestane arm vs. the placebo in combination with exemestane arm (Table 20). There were 3 complete responses (0.6%) and 58 partial responses (12%) in the AFINITOR arm. There were no complete responses and 4 partial responses (1.7%) in the placebo in combination with exemestane arm.

After a median follow-up of 39.3 months, there was no statistically significant difference in OS between the AFINITOR in combination with exemestane arm and the placebo in combination with exemestane arm [HR 0.89 (95% CI: 0.73, 1.10)].

Table 20: Efficacy Results in Hormone-Receptor Positive, HER-2 Negative Breast Cancer in BOLERO-2
Analysis | AFINITOR with Exemestane N = 485 | Placebo with Exemestane N = 239 | Hazard Ratio | p-value
Median progression-free survival (months, 95% CI)
Investigator radiological review | 7.8 (6.9, 8.5) | 3.2 (2.8, 4.1) | 0.45a (0.38, 0.54) | < 0.0001b
Independent radiological review | 11.0 (9.7, 15.0) | 4.1 (2.9, 5.6) | 0.38a (0.3, 0.5) | < 0.0001b
Best overall response (%, 95% CI)
Objective response rate (ORR)c | 12.6% (9.8, 15.9) | 1.7% (0.5, 4.2) | n/ad
aHazard ratio is obtained from the stratified Cox proportional-hazards model by sensitivity to prior hormonal therapy and presence of visceral metastasis.
bp-value is obtained from the one-sided log-rank test stratified by sensitivity to prior hormonal therapy and presence of visceral metastasis.
cObjective response rate = proportion of patients with CR or PR.
dNot applicable.

Figure 1: Kaplan-Meier Curves for Progression-Free Survival by Investigator Radiological Review in Hormone Receptor-Positive, HER-2 Negative Breast Cancer in BOLERO-2

14.2 Neuroendocrine Tumors (NET)

Pancreatic Neuroendocrine Tumors (PNET)

A randomized, double-blind, multicenter trial (RADIANT-3, NCT00510068) of AFINITOR in combination with best supportive care (BSC) compared to placebo in combination with BSC was conducted in patients with locally advanced or metastatic advanced PNET and disease progression within the prior 12 months. Patients were stratified by prior cytotoxic chemotherapy (yes vs. no) and WHO performance status (0 vs. 1 and 2). Treatment with somatostatin analogs was allowed as part of BSC. The major efficacy outcome was PFS evaluated by RECIST. After documented radiological progression, patients randomized to placebo could receive open-label AFINITOR. Other outcome measures included ORR, response duration, and OS.

Patients were randomized 1:1 to receive either AFINITOR 10 mg once daily (n = 207) or placebo (n = 203). Demographics were well balanced (median age 58 years, 55% male, 79% white). Of the 203 patients randomized to BSC, 172 patients (85%) received AFINITOR following documented radiologic progression.

The trial demonstrated a statistically significant improvement in PFS (Table 21 and Figure 2). PFS improvement was observed across all patient subgroups, irrespective of prior somatostatin analog use. The PFS results by investigator radiological review, central radiological review and adjudicated radiological review are shown below in Table 21.

Table 21: Progression-Free Survival Results in PNET in RADIANT-3
Analysis | N | AFINITOR N = 207 | Placebo N = 203 | Hazard Ratio (95% CI) | p-value
 | 410 | Median progression-free survival (months) (95% CI)
Investigator radiological review |  | 11.0 (8.4, 13.9) | 4.6 (3.1, 5.4) | 0.35 (0.27, 0.45) | < 0.001
Central radiological review |  | 13.7 (11.2, 18.8) | 5.7 (5.4, 8.3) | 0.38 (0.28, 0.51) | < 0.001
Adjudicated radiological reviewa |  | 11.4 (10.8, 14.8) | 5.4 (4.3, 5.6) | 0.34 (0.26, 0.44) | < 0.001
aIncludes adjudication for discrepant assessments between investigator radiological review and central radiological review.

Figure 2: Kaplan-Meier Curves for Progression-Free Survival by Investigator Radiological Review in PNET in RADIANT-3

Investigator-determined response rate was 4.8% in the AFINITOR arm and there were no complete responses. Overall Survival (OS) was not statistically significantly different between arms [HR = 0.94 (95% CI 0.73, 1.20); p = 0.30].

NET of Gastrointestinal (GI) or Lung Origin

A randomized, double-blind, multicenter study (RADIANT-4, NCT01524783) of AFINITOR in combination with BSC compared to placebo in combination with BSC was conducted in patients with unresectable, locally advanced or metastatic, well differentiated, non-functional NET of GI (excluding pancreatic) or lung origin. The study required that patients had well-differentiated (low or intermediate grade) histology, no prior or current history of carcinoid symptoms, and evidence of disease progression within 6 months prior to randomization. Patients were randomized 2:1 to receive either AFINITOR 10 mg once daily or placebo, and stratified by prior somatostatin analog use (yes vs. no), tumor origin and WHO performance status (0 vs. 1). The major efficacy outcome measure was PFS based on independent radiological assessment evaluated by RECIST. Additional efficacy outcome measures were OS and ORR.

A total of 302 patients were randomized, 205 to the AFINITOR arm and 97 to the placebo arm. The median age was 63 years (22 to 86 years); 47% were male; 76% were white; 74% had WHO performance status of 0 and 26% had WHO performance status of 1. The most common primary sites of tumor were lung (30%), ileum (24%), and rectum (13%).

The study demonstrated a statistically significant improvement in PFS per independent radiological review (Table 22 and Figure 3). The final OS analysis did not show a statistically significant difference between those patients who received AFINITOR or placebo (HR = 0.90 [95% CI: 0.66, 1.24]).

Table 22: Progression-Free Survival in Neuroendocrine Tumors of Gastrointestinal or Lung Origin in RADIANT-4
 | AFINITOR N = 205 | Placebo N = 97
Progression-Free Survival
Number of Events | 113 (55%) | 65 (67%)
Progressive Disease | 104 (51%) | 60 (62%)
Death | 9 (4%) | 5 (5%)
Median PFS in months (95% CI) | 11.0 (9.2, 13.3) | 3.9 (3.6, 7.4)
Hazard Ratio (95% CI)a | 0.48 (0.35, 0.67)
p-valueb | < 0.001
Overall Response Rate | 2% | 1%
aHazard ratio is obtained from the stratified Cox model.
bp-value is obtained from the stratified log-rank test.

Figure 3: Kaplan-Meier Curves for Progression-Free Survival in NET of GI or Lung Origin in RADIANT-4

Lack of Efficacy in Locally Advanced or Metastatic Functional Carcinoid Tumors

The safety and effectiveness of AFINITOR in patients with locally advanced or metastatic functional carcinoid tumors have not been demonstrated. In a randomized (1:1), double-blind, multicenter trial (RADIANT-2, NCT00412061) in 429 patients with carcinoid tumors, AFINITOR in combination with long-acting octreotide (Sandostatin LAR®) was compared to placebo in combination with long-acting octreotide. After documented radiological progression, patients on the placebo arm could receive AFINITOR; of those randomized to placebo, 67% received open-label AFINITOR in combination with long-acting octreotide. The study did not meet its major efficacy outcome measure of a statistically significant improvement in PFS and the final analysis of OS favored the placebo in combination with long-acting octreotide arm.

14.3 Renal Cell Carcinoma (RCC)

An international, multicenter, randomized, double-blind trial (RECORD-1, NCT00410124) comparing AFINITOR 10 mg once daily and placebo, both in conjunction with BSC, was conducted in patients with metastatic RCC whose disease had progressed despite prior treatment with sunitinib, sorafenib, or both sequentially. Prior therapy with bevacizumab, interleukin 2, or interferon-α was also permitted. Randomization was stratified according to prognostic score and prior anticancer therapy. The major efficacy outcome measure for the trial was PFS evaluated by RECIST, based on a blinded, independent, central radiologic review. After documented radiological progression, patients randomized to placebo could receive open-label AFINITOR. Other outcome measures included OS.

In total, 416 patients were randomized 2:1 to receive AFINITOR (n = 277) or placebo (n = 139). Demographics were well balanced between the arms (median age 61 years; 77% male, 88% white, 74% received prior sunitinib or sorafenib, and 26% received both sequentially).

AFINITOR was superior to placebo for PFS (Table 23 and Figure 4). The treatment effect was similar across prognostic scores and prior sorafenib and/or sunitinib. Final OS results yield a hazard ratio of 0.90 (95% CI: 0.71, 1.14), with no statistically significant difference between the arms. Planned cross-over from placebo due to disease progression to open-label AFINITOR occurred in 80% of the 139 patients and may have confounded the OS benefit.

Table 23: Progression-Free Survival and Objective Response Rate by Central Radiologic Review in RCC in RECORD-1
 | AFINITOR N = 277 | Placebo N = 139 | Hazard Ratio (95% CI) | p-valuea
Median Progression-free Survival (95% CI) | 4.9 months (4.0, 5.5) | 1.9 months (1.8, 1.9) | 0.33 (0.25, 0.43) | < 0.0001
Objective Response Rate | 2% | 0% | n/ab | n/ab
aLog-rank test stratified by prognostic score.
bNot applicable.

Figure 4: Kaplan-Meier Curves for Progression-Free Survival in RCC in RECORD-1

14.4 Tuberous Sclerosis Complex (TSC)-Associated Renal Angiomyolipoma

A randomized (2:1), double-blind, placebo-controlled trial (EXIST-2, NCT00790400) of AFINITOR was conducted in 118 patients with renal angiomyolipoma as a feature of TSC (n = 113) or sporadic lymphangioleiomyomatosis (n = 5). The key eligibility requirements for this trial were at least one angiomyolipoma of ≥ 3 cm in longest diameter on CT/MRI based on local radiology assessment, no immediate indication for surgery, and age ≥ 18 years. Patients received AFINITOR 10 mg or matching placebo orally once daily until disease progression or unacceptable toxicity. CT or MRI scans for disease assessment were obtained at baseline, 12, 24, and 48 weeks and annually thereafter. Clinical and photographic assessment of skin lesions were conducted at baseline and every 12 weeks thereafter until treatment discontinuation. The major efficacy outcome measure was angiomyolipoma response rate based on independent central radiology review, which was defined as a ≥ 50% reduction in angiomyolipoma volume, absence of new angiomyolipoma lesion ≥ 1 cm, absence of kidney volume increase ≥ 20%, and no angiomyolipoma related bleeding of ≥ Grade 2. Key supportive efficacy outcome measures were time to angiomyolipoma progression and skin lesion response rate. The primary analyses of efficacy outcome measures were limited to the blinded treatment period and conducted 6 months after the last patient was randomized. The comparative angiomyolipoma response rate analysis was stratified by use of enzyme-inducing antiepileptic drugs (EIAEDs) at randomization (yes vs. no).

Of the 118 patients enrolled, 79 were randomized to AFINITOR and 39 to placebo. The median age was 31 years (18 to 61 years), 34% were male, and 89% were white. At baseline, 17% of patients were receiving EIAEDs. On central radiology review at baseline, 92% of patients had at least 1 angiomyolipoma of ≥ 3 cm in longest diameter, 29% had angiomyolipomas ≥ 8 cm, 78% had bilateral angiomyolipomas, and 97% had skin lesions. The median values for the sum of all target renal angiomyolipoma lesions at baseline were 85 cm^3 (9 to 1612 cm^3) and 120 cm^3 (3 to 4520 cm^3) in the AFINITOR and placebo arms, respectively. Forty-six (39%) patients had prior renal embolization or nephrectomy. The median duration of follow-up was 8.3 months (0.7 to 24.8 months) at the time of the primary analysis.

The renal angiomyolipoma response rate was statistically significantly higher in AFINITOR-treated patients (Table 24). The median response duration was 5.3+ months (2.3+ to 19.6+ months).

There were 3 patients in the AFINITOR arm and 8 patients in the placebo arm with documented angiomyolipoma progression by central radiologic review (defined as a ≥ 25% increase from nadir in the sum of angiomyolipoma target lesion volumes to a value greater than baseline, appearance of a new angiomyolipoma ≥ 1 cm in longest diameter, an increase in renal volume ≥ 20% from nadir for either kidney and to a value greater than baseline, or Grade ≥ 2 angiomyolipoma-related bleeding). The time to angiomyolipoma progression was statistically significantly longer in the AFINITOR arm (HR 0.08 [95% CI: 0.02, 0.37]; p < 0.0001).

Table 24: Angiomyolipoma Response Rate in TSC-Associated Renal Angiomyolipoma in EXIST-2
 | AFINITOR | Placebo | p-value
 | N = 79 | N = 39
Primary analysis
Angiomyolipoma response ratea - (%) | 41.8 | 0 | < 0.0001
95% CI | (30.8, 53.4) | (0.0, 9.0)
aPer independent central radiology review.

Skin lesion response rates were assessed by local investigators for 77 patients in the AFINITOR arm and 37 patients in the placebo arm who presented with skin lesions at study entry. The skin lesion response rate was statistically significantly higher in the AFINITOR arm (26% vs. 0, p = 0.0011); all skin lesion responses were partial responses, defined as visual improvement in 50% to 99% of all skin lesions durable for at least 8 weeks (Physician's Global Assessment of Clinical Condition).

Patients randomized to placebo were permitted to receive AFINITOR at the time of angiomyolipoma progression or after the time of the primary analysis. After the primary analysis, patients treated with AFINITOR underwent additional follow-up CT or MRI scans to assess tumor status until discontinuation of treatment or completion of 4 years of follow-up after the last patient was randomized. A total of 112 patients (79 randomized to AFINITOR and 33 randomized to placebo) received at least one dose of AFINITOR. The median duration of AFINITOR treatment was 3.9 years (0.5 months to 5.3 years) and the median duration of follow-up was 3.9 years (0.9 months to 5.4 years). During the follow-up period after the primary analysis, 32 patients (in addition to the 33 patients identified at the time of the primary analysis) had an angiomyolipoma response based upon independent central radiology review. Among the 65 responders out of 112 patients, the median time to angiomyolipoma response was 2.9 months (2.6 to 33.8 months). Fourteen percent of the 112 patients treated with AFINITOR had angiomyolipoma progression by the end of the follow-up period. No patient underwent a nephrectomy for angiomyolipoma progression and one patient underwent renal embolization while treated with AFINITOR.

14.5 Tuberous Sclerosis Complex (TSC)-Associated Subependymal Giant Cell Astrocytoma (SEGA)

EXIST-1

A randomized (2:1), double-blind, placebo-controlled trial (EXIST-1, NCT00789828) of AFINITOR was conducted in 117 pediatric and adult patients with SEGA and TSC. Eligible patients had at least one SEGA lesion ≥ 1 cm in longest diameter on MRI based on local radiology assessment and one or more of the following: serial radiological evidence of SEGA growth, a new SEGA lesion ≥ 1 cm in longest diameter, or new or worsening hydrocephalus. Patients randomized to the treatment arm received AFINITOR at a starting dose of 4.5 mg/m^2 daily, with subsequent dose adjustments as needed to achieve and maintain everolimus trough concentrations of 5 to 15 ng/mL as tolerated. AFINITOR or matched placebo continued until disease progression or unacceptable toxicity. MRI scans for disease assessment were obtained at baseline, 12, 24, and 48 weeks, and annually thereafter.

The main efficacy outcome measure was SEGA response rate based on independent central radiology review. SEGA response was defined as a ≥ 50% reduction in the sum of SEGA volume relative to baseline, in the absence of unequivocal worsening of non-target SEGA lesions, a new SEGA lesion ≥ 1 cm, and new or worsening hydrocephalus. The primary analysis of SEGA response rate was limited to the blinded treatment period and conducted 6 months after the last patient was randomized. The analysis of SEGA response rate was stratified by use of enzyme-inducing antiepileptic drugs (EIAEDs) at randomization (yes vs. no).

Of the 117 patients enrolled, 78 were randomized to AFINITOR and 39 to placebo. The median age was 9.5 years (0.8 to 26 years); a total of 20 patients were < 3 years, 54 patients were 3 to < 12 years, 27 patients were 12 to < 18 years, and 16 patients were ≥ 18 years; 57% were male, and 93% were white. At baseline, 18% of patients were receiving EIAEDs. Based on central radiology review at baseline, 98% of patients had at least one SEGA lesion ≥ 1.0 cm in longest diameter, 79% had bilateral SEGAs, 43% had ≥ 2 target SEGA lesions, 26% had growth in or into the inferior surface of the ventricle, 9% had evidence of growth beyond the subependymal tissue adjacent to the ventricle, and 7% had radiographic evidence of hydrocephalus. The median values for the sum of all target SEGA lesions at baseline were 1.63 cm^3 (0.18 to 25.15 cm^3) and 1.30 cm^3 (0.32 to 9.75 cm^3) in the AFINITOR and placebo arms, respectively. Eight (7%) patients had prior SEGA-related surgery. The median duration of follow-up was 8.4 months (4.6 to 17.2 months) at the time of primary analysis.

The SEGA response rate was statistically significantly higher in AFINITOR-treated patients (Table 25). At the time of the primary analysis, all SEGA responses were ongoing and the median duration of response was 5.3 months (2.1 to 8.4 months).

With a median follow-up of 8.4 months, SEGA progression was detected in 15.4% of the 39 patients randomized to receive placebo and none of the 78 patients randomized to receive AFINITOR. No patient in either treatment arm required surgical intervention.

Table 25: Subependymal Giant Cell Astrocytoma Response Rate in TSC-Associated SEGA in EXIST-1
 | AFINITOR | Placebo | p-value
 | N = 78 | N = 39
Primary analysis
SEGA response ratea - (%) | 35 | 0 | < 0.0001
95% CI | 24, 46 | 0, 9
aPer independent central radiology review.

Patients randomized to placebo were permitted to receive AFINITOR at the time of SEGA progression or after the primary analysis, whichever occurred first. After the primary analysis, patients treated with AFINITOR underwent additional follow-up MRI scans to assess tumor status until discontinuation of treatment or completion of 4 years of follow-up after the last patient was randomized. A total of 111 patients (78 patients randomized to AFINITOR and 33 patients randomized to placebo) received at least one dose of AFINITOR. Median duration of AFINITOR treatment and follow-up was 3.9 years (0.2 to 4.9 years).

By four years after the last patient was enrolled, 58% of the 111 patients treated with AFINITOR had a ≥ 50% reduction in SEGA volume relative to baseline, including 27 patients identified at the time of the primary analysis and 37 patients with a SEGA response after the primary analysis. The median time to SEGA response was 5.3 months (2.5 to 33.1 months). Twelve percent of the 111 patients treated with AFINITOR had documented disease progression by the end of the follow-up period and no patient required surgical intervention for SEGA during the study.

Study 2485

Study 2485 (NCT00411619) was an open-label, single-arm trial conducted to evaluate the antitumor activity of AFINITOR 3 mg/m^2/orally once daily in patients with SEGA and TSC. Serial radiological evidence of SEGA growth was required for entry. Tumor assessments were performed every 6 months for 60 months after the last patient was enrolled or disease progression, whichever occurred earlier. The major efficacy outcome measure was the reduction in volume of the largest SEGA lesion with 6 months of treatment, as assessed via independent central radiology review. Progression was defined as an increase in volume of the largest SEGA lesion over baseline that was ≥ 25% over the nadir observed on study.

A total of 28 patients received AFINITOR for a median duration of 5.7 years (5 months to 6.9 years); 82% of the 28 patients remained on AFINITOR for at least 5 years. The median age was 11 years (3 to 34 years), 61% male, 86% white.

At the primary analysis, 32% of the 28 patients (95% CI: 16%, 52%) had an objective response at 6 months, defined as at least a 50% decrease in volume of the largest SEGA lesion. At the completion of the study, the median duration of durable response was 12 months (3 months to 6.3 years).

By 60 months after the last patient was enrolled, 11% of the 28 patients had documented disease progression. No patient developed a new SEGA lesion while on AFINITOR. Nine additional patients were identified as having a ≥ 50% volumetric reduction in their largest SEGA lesion between 1 to 4 years after initiating AFINITOR, including 3 patients who had surgical resection with subsequent regrowth prior to receiving AFINITOR.

14.6 Tuberous Sclerosis Complex (TSC)-Associated Partial-Onset Seizures

The efficacy of AFINITOR DISPERZ as an adjunctive anti-epileptic drug (AED) was evaluated in a randomized, double-blind, multicenter, placebo-controlled study conducted in patients with TSC-associated partial-onset seizures (EXIST-3, NCT01713946). Patients with a history of inadequate control of partial-onset seizures despite treatment with ≥ 2 sequential AED regimens were randomized to receive placebo or AFINITOR DISPERZ once daily at a dose to achieve a low trough (LT) level (3-7 ng/mL) or a high trough (HT) level (9-15 ng/mL). Randomization was stratified by age group (1 to < 6, 6 to < 12, 12 to < 18, ≥ 18 years). The study consisted of 3 phases: an 8-week Baseline observation phase; an 18-week double-blind, placebo-controlled Core phase (6-week titration period and a 12-week maintenance period), and an Extension phase of ≥ 48 weeks. Patients were required to have a diagnosis of TSC per the modified Gomez criteria, and ≥ 16 partial-onset seizures during the Baseline phase while receiving a stable dose of 1 to 3 concomitant AEDs. The starting doses for AFINITOR DISPERZ in the Core phase ranged from 3 to 6 mg/m^2 orally once daily, depending on age, in patients not receiving concomitant CYP3A4/P-gp inducers and from 5 to 9 mg/m^2 orally once daily, depending on age, in patients receiving concomitant CYP3A4/P-gp inducers. During the 6-week titration period, everolimus trough levels were assessed every 2 weeks and up to 3 dose adjustments were allowed to attempt to reach the targeted everolimus trough concentration range.

The major efficacy outcome measure was the percentage reduction in seizure frequency from the Baseline phase, during the maintenance period of the Core phase. Additional efficacy outcome measures included response rate, defined as at least a 50% reduction in seizure frequency from the Baseline phase during the maintenance period of the Core phase, and seizure freedom rate during the maintenance period of the Core phase.

A total of 366 patients were randomized to AFINITOR DISPERZ LT (n = 117), AFINITOR DISPERZ HT (n = 130) or placebo (n = 119). Median age was 10.1 years (2.2 to 56 years); 28% of patients were < 6 years, 31% were 6 to < 12 years, 22% were 12 to < 18 years, and 18% were ≥ 18 years). The majority were white (65%) and male (52%). The most common major features of TSC were cortical tubers (92%), hypomelanotic macules (84%), and subependymal nodules (83%). While 17% of the patients had SEGA, 42% had renal angiomyolipoma, and 9% had both SEGA and renal angiomyolipoma; no patients were receiving treatment with AFINITOR or AFINITOR DISPERZ for these manifestations of TSC. During the Baseline phase, 65% of patients had complex partial seizures, 52% had secondarily generalized seizures, 19% had simple partial seizures, and 2% had generalized onset seizures. The median seizure frequency per week during the Baseline phase was 9.4 for all patients and 47% of patients were receiving 3 AEDs during the Baseline phase. The efficacy results are summarized in Table 26.

Table 26: Percentage Reduction in Seizure Frequency and Response Rate in TSC-Associated Partial-Onset Seizures in EXIST-3
 | AFINITOR DISPERZ |  | Placebo
 | Target of 3-7 ng/mL N = 117 | Target of 9-15 ng/mL N = 130 | N = 119
Seizures per week
Median at Baseline (Min, Max) | 8.6 (1.4, 192.9) | 9.5 (0.3, 218.4) | 10.5 (1.3, 231.7)
Median at Core phasea (Min, Max) | 6.8 (0.0, 193.5) | 4.9 (0.0, 133.7) | 8.5 (0.0, 217.7)
Percentage reduction from Baseline to Core phase (Maintenancea)
Median | 29.3 | 39.6 | 14.9
95% CIb | 18.8, 41.9 | 35.0, 48.7 | 0.1, 21.7
p-valuec | 0.003 | < 0.001
Response rate
Responders, n (%) | 28.2 | 40 | 15.1
95% CId | 20.3, 37.3 | 31.5, 49.0 | 9.2, 22.8
aIf patient discontinued before starting the Maintenance period, then the Titration period is used.
b95% CI of the median based on bootstrap percentiles.
cp-values were for superiority vs. placebo, and obtained from rank ANCOVA with Baseline seizure frequency as covariate, stratified by age subgroup.
dExact 95% CI obtained using Clopper-Pearson method.

15 REFERENCES

1. OSHA Hazardous Drugs. OSHA. http://www.osha.gov/SLTC/hazardousdrugs/index.html.

16 HOW SUPPLIED/STORAGE AND HANDLING

AFINITOR

2.5 mg tablets: White to slightly yellow, elongated tablets with a bevelled edge and engraved with “LCL” on one side and “NVR” on the other; available in:

Blisters of 28 tablets………………………………………………………………………………NDC 0078-0594-51

Each carton contains 4 blister cards of 7 tablets each

5 mg tablets: White to slightly yellow, elongated tablets with a bevelled edge and engraved with “5” on one side and “NVR” on the other; available in:

Blisters of 28 tablets………………………………………………………………………………NDC 0078-0566-51

Each carton contains 4 blister cards of 7 tablets each

7.5 mg tablets: White to slightly yellow, elongated tablets with a bevelled edge and engraved with “7P5” on one side and “NVR” on the other; available in:

Blisters of 28 tablets………………………………………………………………………………NDC 0078-0620-51

Each carton contains 4 blister cards of 7 tablets each

10 mg tablets: White to slightly yellow, elongated tablets with a bevelled edge and engraved with “UHE” on one side and “NVR” on the other; available in:

Blisters of 28 tablets………………………………………………………………………………NDC 0078-0567-51

Each carton contains 4 blister cards of 7 tablets each

AFINITOR DISPERZ

2 mg tablets for oral suspension: White to slightly yellowish, round, flat tablets with a bevelled edge and engraved with “D2” on one side and “NVR” on the other; available in:

Blisters of 28 tablets………………………………………………………………………………NDC 0078-0626-51

Each carton contains 4 blister cards of 7 tablets each

3 mg tablets for oral suspension: White to slightly yellowish, round, flat tablets with a bevelled edge and engraved with “D3” on one side and “NVR” on the other; available in:

Blisters of 28 tablets………………………………………………………………………………NDC 0078-0627-51

Each carton contains 4 blister cards of 7 tablets each

5 mg tablets for oral suspension: White to slightly yellowish, round, flat tablets with a bevelled edge and engraved with “D5” on one side and “NVR” on the other; available in:

Blisters of 28 tablets………………………………………………………………………………NDC 0078-0628-51

Each carton contains 4 blister cards of 7 tablets each

Store at 20°C to 25°C (68°F to 77°F); excursions permitted between 15°C and 30°C (59°F and 86°F). See USP Controlled Room Temperature.

Store in the original container, protect from light and moisture.

Follow special handling and disposal procedures for anti-cancer pharmaceuticals.^1

17 PATIENT COUNSELING INFORMATION

Advise the patient to read the FDA-approved patient labeling (Patient Information and Instructions for Use).

Non-infectious Pneumonitis

Advise patients of the risk of developing non-infectious pneumonitis and to immediately report any new or worsening respiratory symptoms to their healthcare provider [see Warnings and Precautions (5.1)].

Infections

Advise patients that they are more susceptible to infections and that they should immediately report any signs or symptoms of infections to their healthcare provider [see Warnings and Precautions (5.2)].

Hypersensitivity Reactions

Advise patients of the risk of clinically significant hypersensitivity reactions and to promptly contact their healthcare provider or seek emergency care for signs of hypersensitivity reaction, including rash, itching, hives, difficulty breathing or swallowing, flushing, chest pain, or dizziness [see Contraindications (4), Warnings and Precautions (5.3)].

Angioedema with Concomitant Use of ACE Inhibitors

Advise patients to avoid ACE inhibitors and to promptly contact their healthcare provider or seek emergency care for signs or symptoms of angioedema [see Warnings and Precautions (5.4)].

Stomatitis

Advise patients of the risk of stomatitis and to use alcohol-free mouthwashes during treatment [see Warnings and Precautions (5.5)].

Renal Impairment

Advise patients of the risk of developing kidney failure and the need to monitor their kidney function periodically during treatment [see Warnings and Precautions (5.6)].

Risk of Impaired Wound Healing

Advise patients that AFINITOR/AFINITOR DISPERZ may impair wound healing. Advise patients to inform their healthcare provider of any planned surgical procedure [see Warnings and Precautions (5.7)].

Geriatric Patients

Inform patients that in a study conducted in patients with breast cancer, the incidence of deaths and adverse reactions leading to permanent discontinuation was higher in patients ≥ 65 years compared to patients < 65 years [see Warnings and Precautions (5.8), Use in Specific Populations (8.5)].

Metabolic Disorders

Advise patients of the risk of metabolic disorders and the need to monitor glucose and lipids periodically during therapy [see Warnings and Precautions (5.9)].

Myelosuppression

Advise patients of the risk of myelosuppression and the need to monitor CBCs periodically during therapy [see Warnings and Precautions (5.10)].

Risk of Infection or Reduced Immune Response with Vaccination

Advise patients to avoid the use of live vaccines and close contact with those who have received live vaccines [see Warnings and Precautions (5.11)].

Embryo-Fetal Toxicity

Advise females of reproductive potential of the potential risk to a fetus. Advise females of reproductive potential to use effective contraception during treatment and for 8 weeks after the last dose. Advise patients to inform their healthcare provider of a known or suspected pregnancy. Advise males with female partners of reproductive potential to use effective contraception during treatment and for 4 weeks after the last dose [see Warnings and Precautions (5.13), Use in Specific Populations (8.1, 8.3)].

Radiation Sensitization and Radiation Recall

Radiation sensitization and recall can occur in patients treated with radiation prior to, during, or subsequent to AFINITOR/AFINITOR DISPERZ treatment. Advise patients to inform their healthcare provider if they have had or are planning to receive radiation therapy [see Warnings and Precautions (5.12)].

Lactation

Advise women not to breastfeed during treatment with AFINITOR/AFINITOR DISPERZ and for 2 weeks after the last dose [see Use in Specific Populations (8.2)].

Infertility

Advise males and females of reproductive potential of the potential risk for impaired fertility [see Use in Specific Populations (8.3)].

Distributed by:
Novartis Pharmaceuticals Corporation
East Hanover, New Jersey 07936

T2022-07

PATIENT INFORMATION

AFINITOR® (a-fin-it-or)
(everolimus)
tablets

AFINITOR DISPERZ® (a-fin-it-or dis-perz)
(everolimus tablets for oral suspension)

Read this Patient Information leaflet that comes with AFINITOR or AFINITOR DISPERZ before you start taking it and each time you get a refill. There may be new information. This information does not take the place of talking to your healthcare provider about your medical condition or treatment.

What is the most important information I should know about AFINITOR and AFINITOR DISPERZ?
AFINITOR and AFINITOR DISPERZ can cause serious side effects, including:

1. You may develop lung or breathing problems. In some people lung or breathing problems may be severe and can lead to death. Tell your healthcare provider right away if you have any of these symptoms:

- New or worsening cough
- Shortness of breath
- Chest pain
- Difficulty breathing or wheezing

2. You may be more likely to develop an infection, such as pneumonia, or a bacterial, fungal or viral infection. Viral infections may include active hepatitis B in people who have had hepatitis B in the past (reactivation). In some people (including adults and children) these infections may be severe and can lead to death. You may need to be treated as soon as possible.
Tell your healthcare provider right away if you have a temperature of 100.5˚F or above, chills, or do not feel well.
Symptoms of hepatitis B or infection may include the following:

- Fever
- Chills
- Skin rash
- Joint pain and swelling
- Tiredness

- Loss of appetite
- Nausea
- Pale stools or dark urine
- Yellowing of the skin
- Pain in the upper right side of the stomach

3. Severe allergic reactions. Call your healthcare provider or get medical help right away if you get signs and symptoms of a severe allergic reaction, including: rash, itching, hives, flushing, trouble breathing or swallowing, chest pain or dizziness.

4. Possible increased risk for a type of allergic reaction called angioedema, in people who take an Angiotensin-Converting Enzyme (ACE) inhibitor medicine during treatment with AFINITOR or AFINITOR DISPERZ. Talk with your healthcare provider before taking AFINITOR or AFINITOR DISPERZ if you are not sure if you take an ACE inhibitor medicine. Get medical help right away if you have trouble breathing or develop swelling of your tongue, mouth, or throat during treatment with AFINITOR or AFINITOR DISPERZ.

5. Mouth ulcers and sores. Mouth ulcers and sores are common during treatment with AFINITOR or AFINITOR DISPERZ but can also be severe. When you start treatment with AFINITOR or AFINITOR DISPERZ, your healthcare provider may tell you to also start a prescription mouthwash to reduce the likelihood of getting mouth ulcers or sores and to reduce their severity. Follow your healthcare provider’s instructions on how to use this prescription mouthwash. If you develop pain, discomfort, or open sores in your mouth, tell your healthcare provider. Your healthcare provider may tell you to restart this mouthwash or to use a special mouthwash or mouth gel that does not contain alcohol, peroxide, iodine, or thyme.

6. You may develop kidney failure. In some people this may be severe and can lead to death. Your healthcare provider should do tests to check your kidney function before and during your treatment with AFINITOR or AFINITOR DISPERZ.

If you have any of the serious side effects listed above, you may need to stop taking AFINITOR or AFINITOR DISPERZ for a while or use a lower dose. Follow your healthcare provider’s instructions.

What is AFINITOR?
AFINITOR is a prescription medicine used to treat:

- advanced hormone receptor-positive, HER2-negative breast cancer, along with the medicine exemestane, in postmenopausal women who have already received certain other medicines for their cancer.
- adults with a type of pancreatic cancer known as pancreatic neuroendocrine tumor (PNET), that has progressed and cannot be treated with surgery.
- adults with a type of cancer known as neuroendocrine tumor (NET) of the stomach and intestine (gastrointestinal), or lung that has progressed and cannot be treated with surgery.
  AFINITOR is not for use in people with carcinoid tumors that actively produce hormones.
- adults with advanced kidney cancer (renal cell carcinoma or RCC) when certain other medicines have not worked.
- people with the following types of tumors that are seen with a genetic condition called tuberous sclerosis complex (TSC):
  - adults with a kidney tumor called angiomyolipoma, when their kidney tumor does not require surgery right away.
  - adults and children 1 year of age and older with a brain tumor called subependymal giant cell astrocytoma (SEGA) when the tumor cannot be removed completely by surgery.

What is AFINITOR DISPERZ?
AFINITOR DISPERZ is a prescription medicine used to treat:

- adults and children 1 year of age and older with a genetic condition called tuberous sclerosis complex (TSC) who have a brain tumor called subependymal giant cell astrocytoma (SEGA) when the tumor cannot be removed completely by surgery.
- adults and children 2 years of age and older with a genetic condition called tuberous sclerosis complex (TSC) who have certain types of seizures (epilepsy), as an added treatment to other antiepileptic medicines.

It is not known if AFINITOR and AFINITOR DISPERZ are safe and effective in children to treat:

- hormone receptor-positive, HER-2 negative breast cancer
- a type of cancer called neuroendocrine tumors (NET)
- kidney cancer (renal cell carcinoma)
- a kidney tumor called angiomyolipoma, that can happen in children with a genetic condition called tuberous sclerosis complex (TSC).

Do not take AFINITOR or AFINITOR DISPERZ if you have had a severe allergic reaction to everolimus.
Talk to your healthcare provider before taking this medicine if you are allergic to:

- a medicine that contains sirolimus
- a medicine that contains temsirolimus

Ask your healthcare provider if you do not know.

Before taking AFINITOR or AFINITOR DISPERZ, tell your healthcare provider about all of your medical conditions, including if you:

- Have or have had kidney problems
- Have or have had liver problems
- Have diabetes or high blood sugar
- Have high blood cholesterol levels
- Have any infections
- Previously had hepatitis B
- Are scheduled to receive any vaccinations. You should not receive a “live vaccine” or be around people who have recently received a “live vaccine” during your treatment with AFINITOR or AFINITOR DISPERZ. If you are not sure about the type of immunization or vaccine, ask your healthcare provider. For children with TSC and SEGA or certain types of seizures, work with your healthcare provider to complete the recommended childhood series of vaccines before your child starts treatment with AFINITOR or AFINITOR DISPERZ.
- Are pregnant, can become pregnant, or have a partner who can become pregnant. AFINITOR or AFINITOR DISPERZ can cause harm to your unborn baby.
  Females who are able to become pregnant:
  ◦ Your healthcare provider will give you a pregnancy test before you start treatment with AFINITOR or AFINITOR DISPERZ.
  ◦ You should use effective birth control during treatment and for 8 weeks after your last dose of AFINITOR or AFINITOR DISPERZ.
  Males with a female partner, you should use effective birth control during treatment and for 4 weeks after your last dose of AFINITOR or AFINITOR DISPERZ.
  Talk to your healthcare provider about birth control methods that may be right for you during this time. If you become pregnant or think you are pregnant, tell your healthcare provider right away.
- Are breastfeeding or plan to breastfeed. It is not known if AFINITOR or AFINITOR DISPERZ passes into your breast milk. Do not breastfeed during treatment and for 2 weeks after your last dose of AFINITOR or AFINITOR DISPERZ.
- Are planning to have surgery or if you have had a recent surgery. You should stop taking AFINITOR or AFINITOR DISPERZ at least 1 week before planned surgery. See “What are the possible side effects of AFINITOR and AFINITOR DISPERZ?”
- Have received radiation therapy or are planning to receive radiation therapy in the future. See “What are the possible side effects of AFINITOR and AFINITOR DISPERZ?”

Tell your healthcare provider about all of the medicines you take, including prescription and over-the-counter medicines, vitamins, and herbal supplements.
AFINITOR or AFINITOR DISPERZ may affect the way other medicines work, and other medicines can affect how AFINITOR or AFINITOR DISPERZ work. Taking AFINITOR or AFINITOR DISPERZ with other medicines can cause serious side effects.
Know the medicines you take. Keep a list of them and show it to your healthcare provider and pharmacist when you get a new medicine. Especially tell your healthcare provider if you take:

- St. John’s Wort (Hypericum perforatum)
- Medicine for:
  - Fungal infections
  - Bacterial infections
  - Tuberculosis
  - Seizures
  - HIV-AIDS
  - Heart conditions or high blood pressure
- Medicines that weaken your immune system (your body’s ability to fight infections and other problems)

Ask your healthcare provider or pharmacist if you are not sure if your medicine is one of those taken for the conditions listed above. If you are taking any medicines for the conditions listed above, your healthcare provider might need to prescribe a different medicine or your dose of AFINITOR or AFINITOR DISPERZ may need to be changed. You should also tell your healthcare provider before you start taking any new medicine.

How should I take AFINITOR or AFINITOR DISPERZ?

- Your healthcare provider will prescribe the dose of AFINITOR or AFINITOR DISPERZ that is right for you.
- Take AFINITOR or AFINITOR DISPERZ exactly as your healthcare provider tells you to.
- Your healthcare provider may change your dose of AFINITOR or AFINITOR DISPERZ or tell you to temporarily interrupt dosing, if needed.
- Take only AFINITOR or AFINITOR DISPERZ. Do not mix AFINITOR and AFINITOR DISPERZ together.
- Use scissors to open the blister pack.
- Take AFINITOR or AFINITOR DISPERZ 1 time each day at about the same time.
- Take AFINITOR or AFINITOR DISPERZ the same way each time, either with food or without food.
- If you take too much AFINITOR or AFINITOR DISPERZ, contact your healthcare provider or go to the nearest hospital emergency room right away. Take the pack of AFINITOR or AFINITOR DISPERZ with you.
- If you miss a dose of AFINITOR or AFINITOR DISPERZ, you may take it if it is less than 6 hours after the time you normally take it. If it is more than 6 hours after you normally take your AFINITOR or AFINITOR DISPERZ, skip the dose for that day. The next day, take AFINITOR or AFINITOR DISPERZ at your usual time. Do not take 2 doses to make up for a missed dose. If you are not sure about what to do, call your healthcare provider.
- You should have blood tests before you start AFINITOR or AFINITOR DISPERZ and as needed during your treatment. These will include tests to check your blood cell count, kidney and liver function, cholesterol, and blood sugar levels.
- If you take AFINITOR or AFINITOR DISPERZ to treat SEGA or AFINITOR DISPERZ to treat certain types of seizures with TSC, you will also need to have blood tests regularly to measure how much medicine is in your blood. This will help your healthcare provider decide how much AFINITOR or AFINITOR DISPERZ you need to take.

AFINITOR:

- Swallow AFINITOR tablets whole with a glass of water. Do not take any tablet that is broken or crushed.

AFINITOR DISPERZ:

- If your healthcare provider prescribes AFINITOR DISPERZ for you, see the “Instructions for Use” that comes with your medicine for instructions on how to prepare and take your dose.
- Each dose of AFINITOR DISPERZ must be prepared as a suspension before it is given.
- AFINITOR DISPERZ can cause harm to an unborn baby. When possible, the suspension should be prepared by an adult who is not pregnant or planning to become pregnant.
- Wear gloves to avoid possible contact with everolimus when preparing suspensions of AFINITOR DISPERZ for another person.

What should I avoid while taking AFINITOR or AFINITOR DISPERZ?
You should not drink grapefruit juice or eat grapefruit during your treatment with AFINITOR or AFINITOR DISPERZ. It may make the amount of AFINITOR or AFINITOR DISPERZ in your blood increase to a harmful level.

What are the possible side effects of AFINITOR or AFINITOR DISPERZ?
AFINITOR and AFINITOR DISPERZ can cause serious side effects, including:

- See “What is the most important information I should know about AFINITOR and AFINITOR DISPERZ?” for more information.
- Risk of wound healing problems. Wounds may not heal properly during AFINITOR and AFINITOR DISPERZ treatment. Tell your healthcare provider if you plan to have any surgery before starting or during treatment with AFINITOR and AFINITOR DISPERZ.
  - You should stop taking AFINITOR and AFINITOR DISPERZ at least 1 week before planned surgery.
  - Your healthcare provider should tell you when you may start taking AFINITOR and AFINITOR DISPERZ again after surgery.
- Increased blood sugar and fat (cholesterol and triglyceride) levels in the blood. Your healthcare provider should do blood tests to check your fasting blood sugar, cholesterol, and triglyceride levels in the blood before you start and during treatment with AFINITOR or AFINITOR DISPERZ.
- Decreased blood cell counts. AFINITOR and AFINITOR DISPERZ can cause you to have decreased red blood cells, white blood cells, and platelets. Your healthcare provider should do blood tests to check your blood cell counts before you start and during treatment with AFINITOR or AFINITOR DISPERZ.
- Worsening side effects from radiation treatment, that can sometimes be severe. Tell your healthcare provider if you have had or are planning to receive radiation therapy.

The most common side effects of AFINITOR in people with advanced hormone receptor-positive, HER2-negative breast cancer, advanced neuroendocrine tumors of the pancreas, stomach and intestine (gastrointestinal) or lung, and advanced kidney cancer include:

- Infections
- Rash
- Feeling weak or tired
- Diarrhea
- Swelling of arms, hands, feet, ankles, face, or other parts of the body

- Stomach-area (abdominal) pain
- Nausea
- Fever
- Cough
- Headache
- Decreased appetite

The most common side effects of AFINITOR and AFINITOR DISPERZ in people who have SEGA, renal angiomyolipoma, or certain types of seizures with TSC include respiratory tract infections.

Other side effects that may occur with AFINITOR and AFINITOR DISPERZ:

- Absence of menstrual periods (menstruation). You may miss 1 or more menstrual periods. Tell your healthcare provider if this happens.
- AFINITOR and AFINITOR DISPERZ may affect fertility in females and may affect your ability to become pregnant. Talk to your healthcare provider if this is a concern for you.
- AFINITOR and AFINITOR DISPERZ may affect fertility in males and may affect your ability to father a child. Talk to your healthcare provider if this is a concern for you.

Tell your healthcare provider if you have any side effect that bothers you or does not go away.

These are not all the possible side effects of AFINITOR and AFINITOR DISPERZ. For more information, ask your healthcare provider or pharmacist.

Call your doctor for medical advice about side effects. You may report side effects to FDA at 1-800-FDA-1088.

How should I store AFINITOR or AFINITOR DISPERZ?

- Store AFINITOR or AFINITOR DISPERZ at room temperature, between 68°F to 77°F (20°C to 25°C).
- Keep AFINITOR or AFINITOR DISPERZ in the pack it comes in.
- Open the blister pack just before taking AFINITOR or AFINITOR DISPERZ.
- Keep AFINITOR or AFINITOR DISPERZ dry and away from light.
- Do not use AFINITOR or AFINITOR DISPERZ that is out of date or no longer needed.
  Keep AFINITOR or AFINITOR DISPERZ and all medicines out of the reach of children.

General information about the safe and effective use of AFINITOR and AFINITOR DISPERZ.

Medicines are sometimes prescribed for purposes other than those listed in a Patient Information leaflet. Do not use AFINITOR or AFINITOR DISPERZ for a condition for which it was not prescribed. Do not give AFINITOR or AFINITOR DISPERZ to other people, even if they have the same problem you have. It may harm them. This leaflet summarizes the most important information about AFINITOR and AFINITOR DISPERZ. If you would like more information, talk with your healthcare provider. You can ask your healthcare provider or pharmacist for information written for healthcare professionals.

What are the ingredients in AFINITOR?

Active ingredient: everolimus.
Inactive ingredients: anhydrous lactose, butylated hydroxytoluene, crospovidone, hypromellose, lactose monohydrate, and magnesium stearate.

What are the ingredients in AFINITOR DISPERZ?

Active ingredient: everolimus.
Inactive ingredients: butylated hydroxytoluene, colloidal silicon dioxide, crospovidone, hypromellose, lactose monohydrate, magnesium stearate, mannitol, and microcrystalline cellulose.

Distributed by:
Novartis Pharmaceuticals Corporation
East Hanover, New Jersey 07936
The brands listed are the trademarks or register marks of their respective owners and are not trademarks or register marks of Novartis.
© Novartis
For more information call 1-888-669-6682 or go to www.AFINITOR.com.

This Patient Information has been approved by the U.S. Food and Drug Administration.

Revised: January 2025

T2025-02

Instructions For Use
AFINITOR (a-fin-it-or) DISPERZ® (dis-perz)
(everolimus tablets for oral suspension)

Read these Instructions for Use for AFINITOR DISPERZ before you start taking it and each time you get a refill. There may be new information. This information does not take the place of talking to your healthcare provider about your medical condition or treatment.

Important Information:

- Take AFINITOR DISPERZ as a suspension only. AFINITOR DISPERZ is prepared as a suspension of undissolved medicine that is mixed with water, and then it is taken by mouth. Do not chew, crush, or swallow AFINITOR DISPERZ whole.
- AFINITOR DISPERZ can cause harm to an unborn baby. When possible, the suspension should be prepared by an adult who is not pregnant or planning to become pregnant.
- Keep AFINITOR DISPERZ and the prepared suspension out of the reach of children.
- Anyone who prepares suspensions of AFINITOR DISPERZ for another person should wear gloves to avoid possible contact with the drug.
- Only use water with AFINITOR DISPERZ to prepare the suspension. Do not prepare the suspension with juice or any other liquids.
- The suspension must be given right away. If you do not give the dose within 60 minutes after it has been prepared, throw away the dose and prepare a new dose of AFINITOR DISPERZ.
- Before starting to prepare the suspension, collect all of the supplies that you will need to prepare and take the suspension. Do not use any of these supplies for purposes other than preparing and taking the AFINITOR DISPERZ suspension.

Supplies needed to prepare the suspension in an oral syringe:

- Blister card with AFINITOR DISPERZ
- Scissors to open the blister card
- Disposable gloves (for one time use)
- 2 clean drinking glasses
- Approximately 30 mL of water
- 10 mL oral syringe (for one time use) (see Figure A)
- Paper towels

Figure A

Supplies needed to prepare the suspension in a small drinking glass:

- Blister card with AFINITOR DISPERZ
- Scissors to open the blister card
- Disposable gloves (for one time use)
- 30 mL dose cup for measuring water (you can ask your pharmacist for this)
- 1 clean drinking glass (maximum size 100 mL)
- Water to prepare the suspension
- Spoon for stirring
- Paper towels

Preparing a dose of AFINITOR DISPERZ suspension using an oral syringe:

Step 1: Prepare a clean, flat work surface that is away from where you prepare and eat food. Place a clean paper towel on the work surface. Place the needed supplies on the paper towel.

Step 2: Wash and dry your hands well before preparing the medicine (see Figure B).

Figure B

Step 3: If preparing the AFINITOR DISPERZ suspension for another person, put on disposable gloves (see Figure C).

Figure C

Step 4: Take a 10 mL oral syringe and pull back on the plunger. Remove the plunger from the barrel of the syringe (see Figure D).

Figure D

Step 5: Use scissors to open the blister card along the dotted line (see Figure E) and remove the prescribed number of AFINITOR DISPERZ tablets for oral suspension from the blister card. Place them into the barrel of the oral syringe (see Figure F).

Figure E

Figure F

- Doses of up to 10 mg can be prepared with the oral syringe. If your total prescribed dose is more than 10 mg, you will need to split the dose. Follow steps 4 through 17 for the first half of the dose. Then repeat steps 4 through 17 for the second half of the dose. Do not prepare a dose of more than 10 mg in one syringe. Ask your pharmacist or healthcare provider if you are not sure what to do.

Step 6: Re-insert the plunger into the barrel of the oral syringe (see Figure G) and push the plunger in until it comes into contact with the AFINITOR DISPERZ tablets for oral suspension (see Figure H).

Figure G

Figure H

Step 7: Fill a small drinking glass with about 30 mL of water. Insert the tip of the oral syringe into the water. Then slowly pull back on the plunger until the syringe is about half full of water and all the tablets are covered by water (see Figure I).

Figure I

Step 8: Hold the oral syringe with the tip pointing up. Pull back on the plunger to draw back about 4 mL of air (see Figure J).

Figure J

Step 9: Place the filled oral syringe in the clean, empty glass with the tip pointing up. Wait 3 minutes to allow AFINITOR DISPERZ to break apart (see Figure K).

Figure K

Step 10: Slowly turn the oral syringe up and down five times just before giving the dose (see Figure L). Do not shake the syringe.

Figure L

Step 11: Hold the oral syringe in an upright position (with the tip up). Carefully remove most of the air by pushing up gently on the plunger (see Figure M).

Figure M

Step 12: Give the full contents of the oral syringe slowly and gently into the mouth right away, within 60 minutes of preparing it (see Figure N). Carefully remove the syringe from the mouth. Continue with steps 13 through 17 to make sure that the entire dose of medicine is given.

Figure N

Step 13: Insert the tip of the oral syringe into the drinking glass that is filled with water, and pull up about 5 mL of water by slowly pulling back on the plunger (see Figure O).

Figure O

Step 14: Hold the oral syringe with the tip pointing up and use the plunger to draw back about 4 mL of air (see Figure P).

Figure P

Step 15: With the tip of the syringe still pointing up, swirl the contents by gently rotating the syringe in a circular motion (see Figure Q).

Figure Q

Step 16: Hold the oral syringe in an upright position (with the tip up). Carefully remove most of the air by pushing up gently on the plunger (see Figure R).

Figure R

Step 17: Give the full contents of the oral syringe slowly and gently into the mouth by pushing on the plunger (see Figure S). Carefully remove the syringe from the mouth.

Figure S

If the total prescribed dose is more than 10 mg, repeat steps 4 through 17 to finish giving the dose.

Step 18: Throw away the oral syringe, paper towel, and used gloves in your household trash.

Step 19: Wash your hands.

Preparing a dose of AFINITOR DISPERZ suspension using a small drinking glass:

Step 1: Prepare a clean, flat work surface that is away from where you prepare and eat food. Place a clean paper towel on the work surface. Place the needed supplies on the paper towel.

Step 2: Wash and dry your hands before preparing the medicine (see Figure T).

Figure T

Step 3: If preparing the AFINITOR DISPERZ suspension for another person, put on disposable gloves (see Figure U).

Figure U

Step 4: Add about 25 mL of water to the 30 mL dose cup. The amount of water added does not need to be exact (see Figure V).

Figure V

Step 5: Pour the water from the dose cup into a small drinking glass (maximum size 100 mL) (see Figure W).

Figure W

- Doses up to 10 mg can be prepared in the small drinking glass. If your total prescribed dose is more than 10 mg, you will need to split the dose. Follow steps 4 through 10 for the first half of the dose. Then repeat steps 4 through 10 for the second half of the dose. Ask your pharmacist or healthcare provider if you are not sure what to do.

Step 6: Use scissors to open the blister card along the dotted line (see Figure X) and remove the prescribed number of AFINITOR DISPERZ tablets for oral suspension from the blister card.

Figure X

Step 7: Add the prescribed number of AFINITOR DISPERZ tablets for oral suspension into the water (see Figure Y).

Figure Y

Step 8: Wait 3 minutes to allow AFINITOR DISPERZ tablets for oral suspension to break apart (see Figure Z).

Figure Z

Step 9: Gently stir the contents of the glass with a spoon and place the spoon back on the paper towel (see Figure AA). Drink the full amount of the suspension right away, within 60 minutes of preparing it (see Figure BB).

Figure AA

Figure BB

Step 10: Refill the glass with the same amount of water (about 25 mL). Stir the contents with the same spoon and place the spoon back on the paper towel (see Figure CC). Drink the full amount right away so that you take any remaining medicine (see Figure DD).

Figure CC

Figure DD

If your total prescribed dose is more than 10 mg, repeat steps 4 through 10 to finish taking your dose.

Step 11: Wash the glass and the spoon thoroughly with water. Wipe the glass and spoon with a clean paper towel and store them in a dry and clean place until your next dose of AFINITOR DISPERZ (see Figure EE).

Figure EE

Step 12: Throw away the used paper towel and gloves in your household trash.

Step 13: Wash your hands.

How should I store AFINITOR DISPERZ?

- Store AFINITOR DISPERZ at room temperature, between 68°F to 77°F (20°C to 25°C).
- Keep AFINITOR DISPERZ in the pack it comes in.
- Open the blister pack just before taking AFINITOR DISPERZ.
- Keep AFINITOR DISPERZ dry and away from light.
- Do not use AFINITOR DISPERZ that is out of date or no longer needed.

Keep AFINITOR DISPERZ and all medicines out of the reach of children.

This Instructions for Use has been approved by the U.S. Food and Drug Administration.

Distributed by:
Novartis Pharmaceuticals Corporation
East Hanover, New Jersey 07936

T2018-82
June 2018

PRINCIPAL DISPLAY PANEL

NDC 0078-0594-51

Rx only

28 Tablets

Carton contains 4 individual blister cards of 7 tablets.

AFINITOR®
(everolimus) tablets

Each tablet contains

2.5 mg

everolimus

NOVARTIS

PRINCIPAL DISPLAY PANEL

NDC 0078-0566-51

Rx only

28 Tablets

Carton contains 4 individual blister cards of 7 tablets.

AFINITOR®
(everolimus) tablets

Each tablet contains

5 mg

everolimus

NOVARTIS

PRINCIPAL DISPLAY PANEL

NDC 0078-0620-51

Rx only

28 Tablets

Carton contains 4 individual blister cards of 7 tablets.

AFINITOR®
(everolimus) tablets

Each tablet contains

7.5 mg

everolimus

NOVARTIS

PRINCIPAL DISPLAY PANEL

NDC 0078-0567-51

Rx only

28 Tablets

Carton contains 4 individual blister cards of 7 tablets.

AFINITOR®
(everolimus) tablets

Each tablet contains

10 mg

everolimus

NOVARTIS

PRINCIPAL DISPLAY PANEL

NDC 0078-0626-51

Rx only

28 Tablets for Oral Suspension

Carton contains 4 individual blister cards of 7 tablets.

AFINITOR DISPERZ®
(everolimus tablets for oral suspension)

2 mg

TABLETS MUST BE DISPERSED IN WATER.

TABLETS MUST NOT BE SWALLOWED WHOLE, CHEWED OR CRUSHED.

Each tablet contains 2 mg everolimus

NOVARTIS

PRINCIPAL DISPLAY PANEL

NDC 0078-0627-51

Rx only

28 Tablets for Oral Suspension

Carton contains 4 individual blister cards of 7 tablets.

AFINITOR DISPERZ®
(everolimus tablets for oral suspension)

3 mg

TABLETS MUST BE DISPERSED IN WATER.

TABLETS MUST NOT BE SWALLOWED WHOLE, CHEWED OR CRUSHED.

Each tablet contains 3 mg everolimus

NOVARTIS

PRINCIPAL DISPLAY PANEL

NDC 0078-0628-51

Rx only

28 Tablets for Oral Suspension

Carton contains 4 individual blister cards of 7 tablets.

AFINITOR DISPERZ®
(everolimus tablets for oral suspension)

5 mg

TABLETS MUST BE DISPERSED IN WATER.

TABLETS MUST NOT BE SWALLOWED WHOLE, CHEWED OR CRUSHED.

Each tablet contains 5 mg everolimus

NOVARTIS